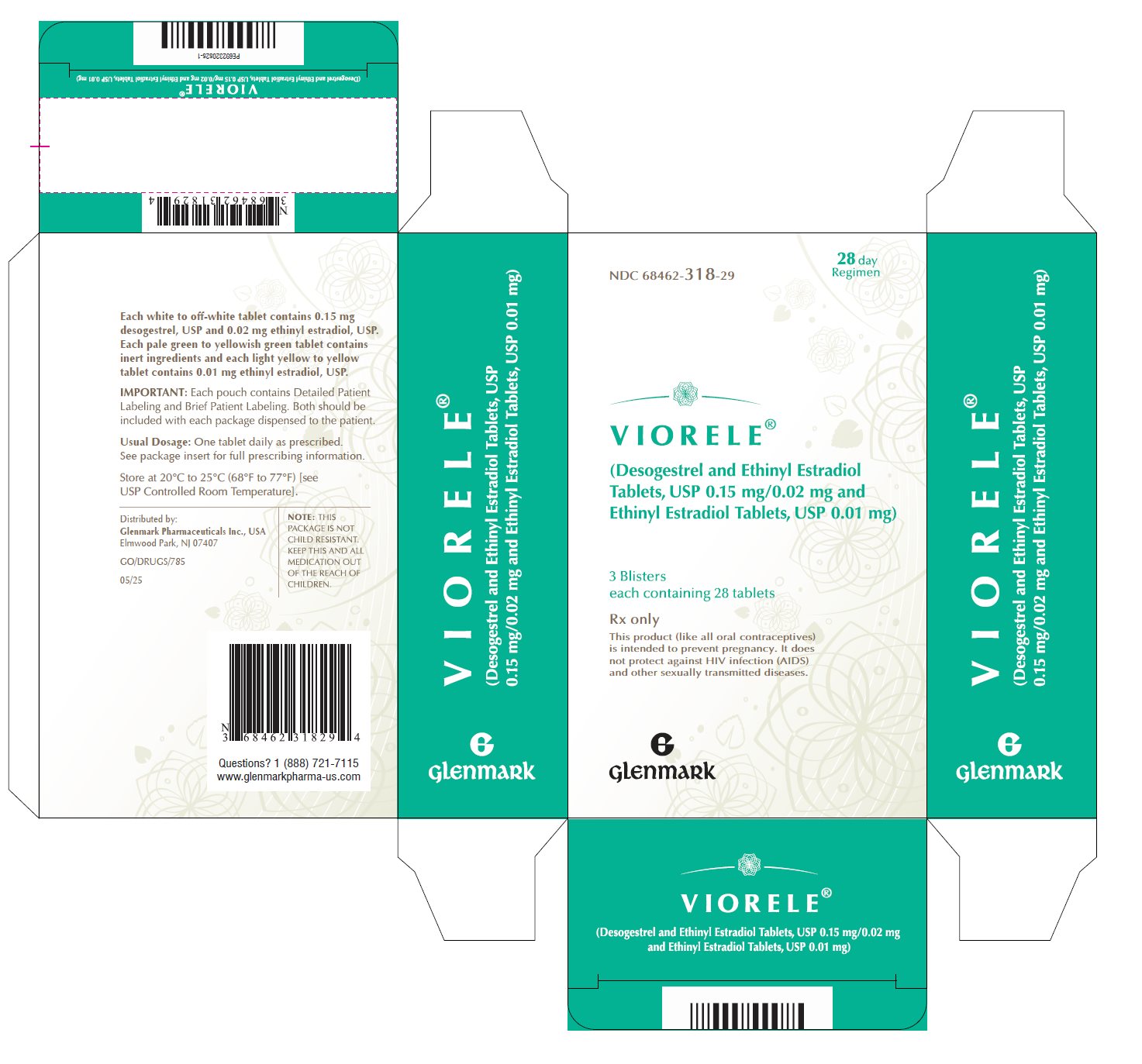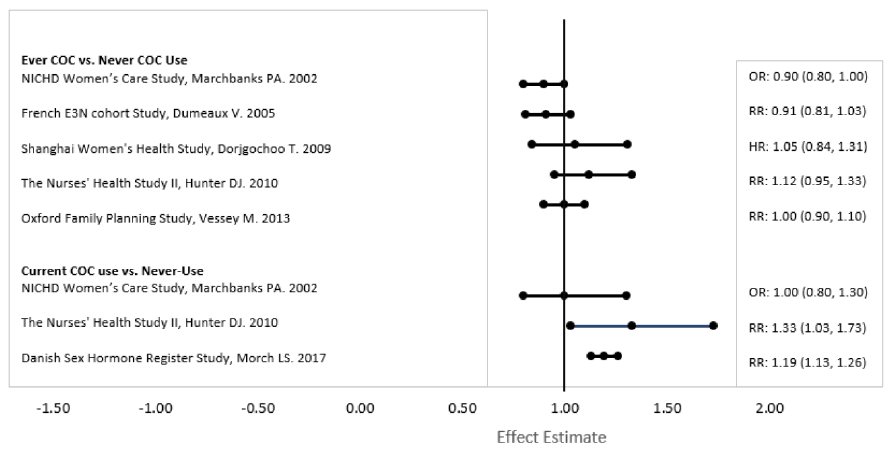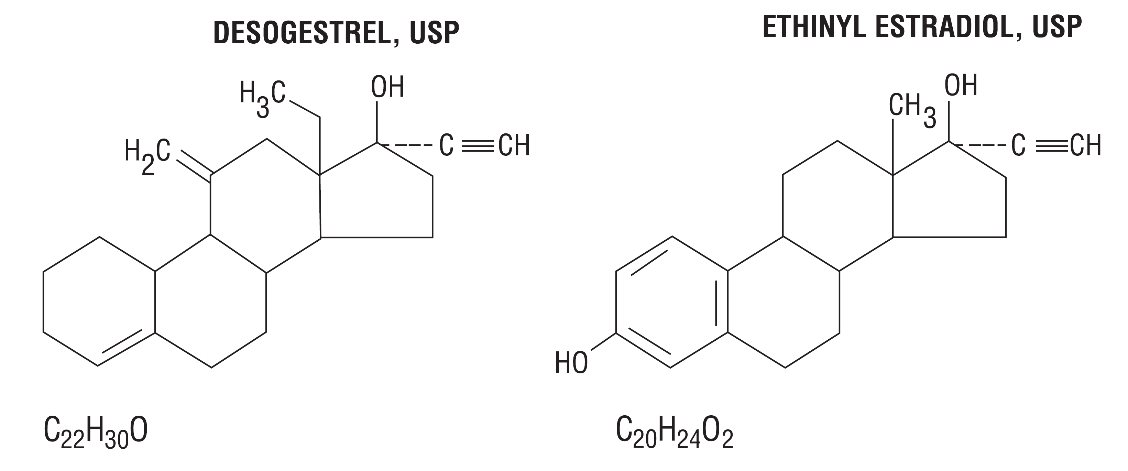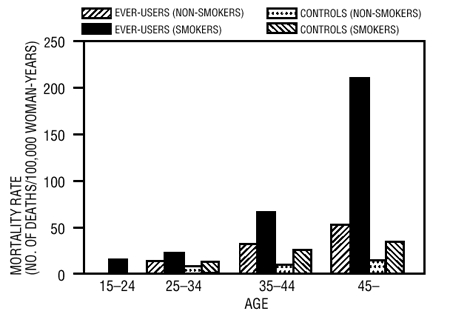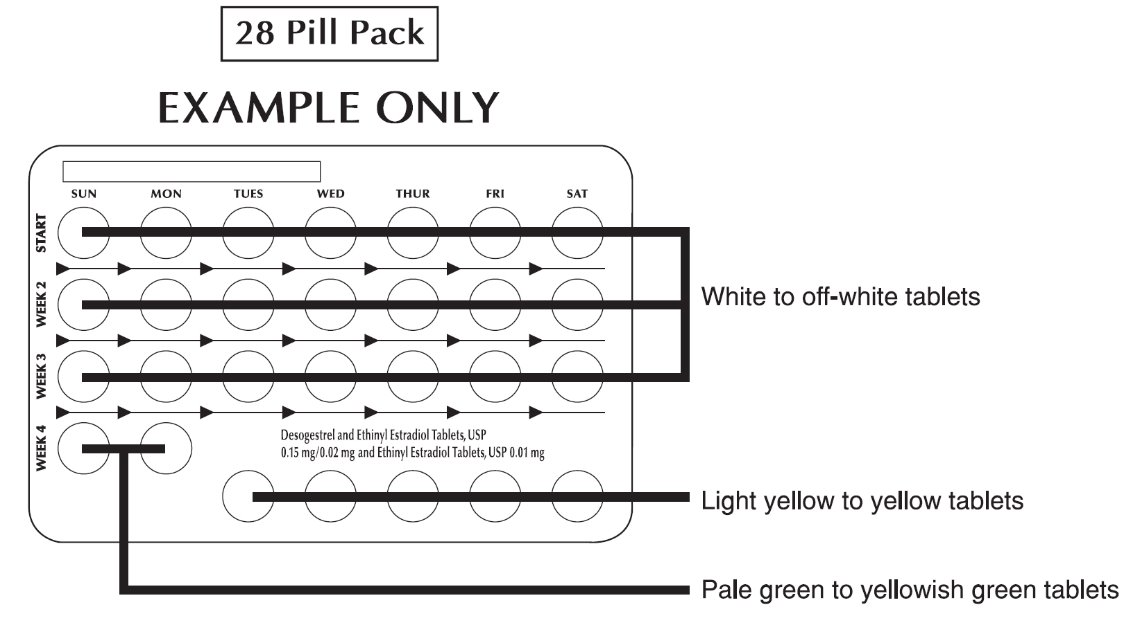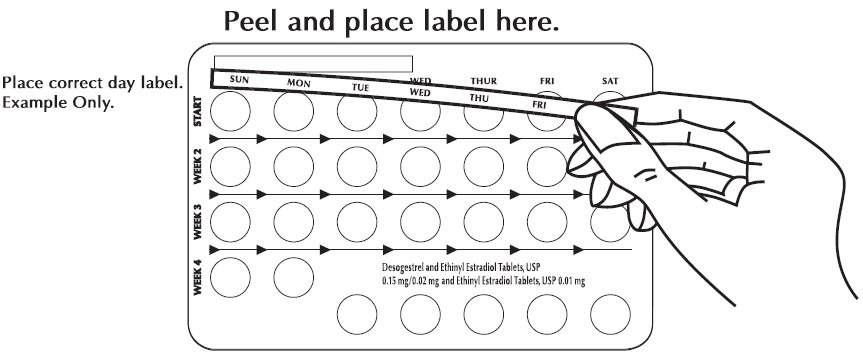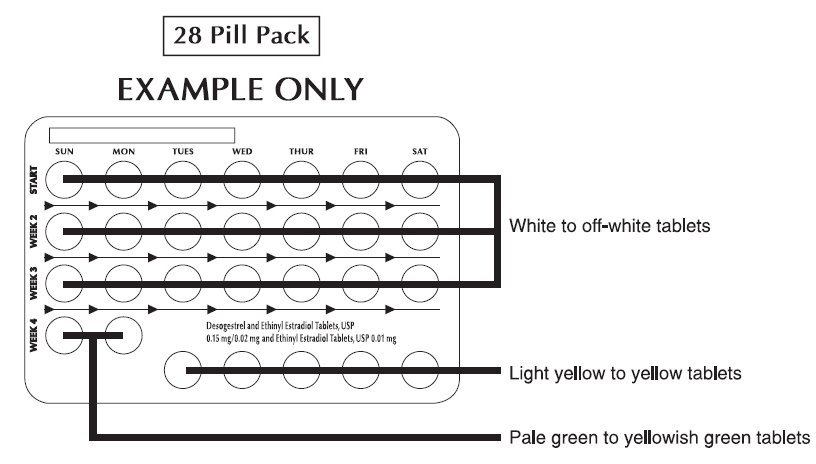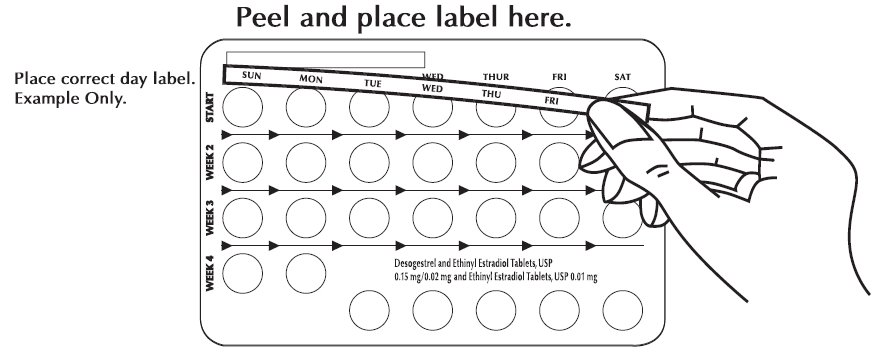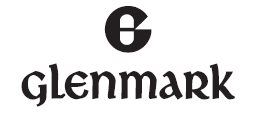 DRUG LABEL: VIORELE
NDC: 68462-318 | Form: KIT | Route: ORAL
Manufacturer: Glenmark Pharmaceuticals Inc., USA
Category: prescription | Type: HUMAN PRESCRIPTION DRUG LABEL
Date: 20260131

ACTIVE INGREDIENTS: DESOGESTREL 0.15 mg/1 1; ETHINYL ESTRADIOL 0.02 mg/1 1; ETHINYL ESTRADIOL 0.01 mg/1 1
INACTIVE INGREDIENTS: .ALPHA.-TOCOPHEROL; STARCH, POTATO; POVIDONE K30; ISOPROPYL ALCOHOL; SILICON DIOXIDE; STEARIC ACID; LACTOSE, UNSPECIFIED FORM; HYPROMELLOSE, UNSPECIFIED; TITANIUM DIOXIDE; POLYETHYLENE GLYCOL 400; TALC; LACTOSE, UNSPECIFIED FORM; STARCH, CORN; MAGNESIUM STEARATE; HYPROMELLOSE, UNSPECIFIED; TITANIUM DIOXIDE; POLYETHYLENE GLYCOL 400; TALC; FERRIC OXIDE YELLOW; FD&C BLUE NO. 2; .ALPHA.-TOCOPHEROL; LACTOSE, UNSPECIFIED FORM; STARCH, POTATO; POVIDONE K30; ISOPROPYL ALCOHOL; SILICON DIOXIDE; MAGNESIUM STEARATE; HYPROMELLOSE, UNSPECIFIED; TITANIUM DIOXIDE; POLYETHYLENE GLYCOL 400; TALC; FERRIC OXIDE YELLOW

VIORELE® (Desogestrel and Ethinyl Estradiol Tablets, USP 0.15 mg/0.02 mg and Ethinyl Estradiol Tablets, USP 0.01 mg)
Rx only

WARNING: CIGARETTE SMOKING AND SERIOUS CARDIOVASCULAR EVENTS

Cigarette smoking increases the risk of serious cardiovascular events from combination oral contraceptive (COC) use. This risk increases with age, particularly in women over 35 years of age, and with the number of cigarettes smoked. For this reason, COCs, including VIORELE, are contraindicated in women who are over 35 years of age and smoke (see CONTRAINDICATIONS and WARNINGS).

DESCRIPTION

VIORELE® (desogestrel and ethinyl estradiol tablets, USP and ethinyl estradiol tablets, USP) provides an oral contraceptive regimen of 21 white to off-white, round tablets each containing 0.15 mg desogestrel, USP (13-ethyl-11- methylene-18,19-dinor-17 alpha-pregn- 4-en- 20-yn-17-ol), 0.02 mg ethinyl estradiol, USP (19-nor-17 alpha-pregna-1,3,5 (10)-trien-20-yne-3,17-diol), and inactive ingredients which include vitamin E, potato starch, povidone, isopropyl alcohol, colloidal silicon dioxide, stearic acid, lactose, hypromellose, titanium dioxide, macrogol, talc, followed by 2 inert pale green to yellowish green, round tablets with following inactive ingredients: lactose, starch, magnesium stearate, hypromellose, titanium dioxide, macrogol, talc, iron oxide yellow, FD&C blue No. 2 indigo carmine aluminum lake. VIORELE® also contains 5 light yellow to yellow, round tablets containing 0.01 mg ethinyl estradiol, USP (19-nor-17 alpha-pregna-1,3,5 (10)-trien-20-yne-3, 17-diol) and inactive ingredients which include vitamin E, lactose, potato starch, povidone, isopropyl alcohol, colloidal silicon dioxide, magnesium stearate, hypromellose, titanium dioxide, macrogol, talc, iron oxide yellow. The molecular weights for desogestrel, USP and ethinyl estradiol, USP are 310.48 g/mol and 296.40 g/mol respectively. The structural formulas are as follows:

CLINICAL PHARMACOLOGY

Combination oral contraceptives act by suppression of gonadotropins. Although the primary mechanism of this action is inhibition of ovulation, other alterations include changes in the cervical mucus (which increase the difficulty of sperm entry into the uterus) and the endometrium (which reduce the likelihood of implantation).

Receptor binding studies, as well as studies in animals, have shown that etonogestrel, the biologically active metabolite of desogestrel, combines high progestational activity with minimal intrinsic androgenicity (91, 92). The relevance of this latter finding in humans is unknown.

Pharmacokinetics

Absorption

Desogestrel is rapidly and almost completely absorbed and converted into etonogestrel, its biologically active metabolite. Following oral administration, the relative bioavailability of desogestrel compared to a solution, as measured by serum levels of etonogestrel, is approximately 100%. VIORELE® provides two different regimens of ethinyl estradiol; 0.02 mg in the combination tablet [white to off-white] as well as 0.01 mg in the light yellow to yellow tablet. Ethinyl estradiol is rapidly and almost completely absorbed. After a single dose of VIORELE® combination tablet [white to off-white], the relative bioavailability of ethinyl estradiol is approximately 93% while the relative bioavailability of the 0.01 mg tablet [light yellow to yellow] is 99%. The effect of food on the bioavailability of VIORELE® following oral administration has not been evaluated.

The pharmacokinetics of etonogestrel and ethinyl estradiol following multiple dose administration of desogestrel/ethinyl estradiol and ethinyl estradiol tablets were determined during the third cycle in 17 subjects. Plasma concentrations of etonogestrel and ethinyl estradiol reached steady-state by Day 21. The AUC(0-24) for etonogestrel at steady-state on Day 21 was approximately 2.2 times higher than AUC(0-24) on Day 1 of the third cycle. The pharmacokinetic parameters of etonogestrel and ethinyl estradiol during the third cycle following multiple dose administration of desogestrel/ethinyl estradiol and ethinyl estradiol tablets are summarized in Table I.

TABLE I: MEAN (SD) PHARMACOKINETIC PARAMETERS OF DESOGESTREL/ETHINYL ESTRADIOL AND ETHINYL ESTRADIOL OVER A 28-DAY DOSING PERIOD IN THE THIRD CYCLE (n=17).

Etonogestrel
Day | Dosea; mg | Cmax; pg/mL | Tmax; h | t½; h | AUC0-24; pg/mL•hr | CL/F; L/h
1 | 0.15 | 2503.6 (987.6) | 2.4 (1) | 29.8 (16.3) | 17,832 (5674) | 5.4 (2.5)
21 | 0.15 | 4091.2 (1186.2) | 1.6 (0.7) | 27.8 (7.2) | 39,391 (12,134) | 4.4 (1.4)
a Desogestrel
Ethinyl Estradiol
Day | Dose; mg | Cmax; pg/mL | Tmax; h | t½; h | AUC0-24 pg/mL•hr | CL/F; L/h
1 | 0.02 | 51.9 (15.4) | 2.9 (1.2) | 16.5 (4.8) | 566 (173)a | 25.7 (9.1)
21 | 0.02 | 62.2 (25.9) | 2 (0.8) | 23.9 (25.5) | 597 (127)a | 35.1 (8.2)
24 | 0.01 | 24.6 (10.8) | 2.4 (1) | 18.8 (10.3) | 246 (65) | 43.6 (12.2)
28 | 0.01 | 35.3 (27.5) | 2.1 (1.3) | 18.9 (8.3) | 312 (62) | 33.2 (6.6)

a n=16

Cmax - measured peak concentration

Tmax - observed time of peak concentration

t½ - elimination half-life, calculated by 0.693/Kelim

AUC0-24 - area under the concentration-time curve calculated by the linear trapezoidal rule (Time 0 to 24 hours)

CL/F - apparent clearance

Distribution

Etonogestrel, the active metabolite of desogestrel, was found to be 99% protein bound, primarily to sex hormone-binding globulin (SHBG). Ethinyl estradiol is approximately 98.3% bound, mainly to plasma albumin. Ethinyl estradiol does not bind to SHBG, but induces SHBG synthesis. Desogestrel, in combination with ethinyl estradiol, does not counteract the estrogen-induced increase in SHBG, resulting in lower serum levels of free testosterone (96-99).

Metabolism

Desogestrel: Desogestrel is rapidly and completely metabolized by hydroxylation in the intestinal mucosa and on first pass through the liver to etonogestrel. Other metabolites (i.e., 3α-OH-desogestrel, 3β-OH-desogestrel, and 3α-OH-5α-H-desogestrel) with no pharmacologic actions also have been identified and these metabolites may undergo glucuronide and sulfate conjugation.

Ethinyl estradiol: Ethinyl estradiol is subject to a significant degree of presystemic conjugation (phase II metabolism). Ethinyl estradiol escaping gut wall conjugation undergoes phase I metabolism and hepatic conjugation (phase II metabolism). Major phase I metabolites are 2-OH-ethinyl estradiol and 2-methoxy-ethinyl estradiol. Sulfate and glucuronide conjugates of both ethinyl estradiol and phase I metabolites, which are excreted in bile, can undergo enterohepatic circulation.

Excretion

Etonogestrel and ethinyl estradiol are excreted in urine, bile, and feces. At steady state, on Day 21, the elimination half-life of etonogestrel is 27.8±7.2 hours and the elimination half-life of ethinyl estradiol for the combination tablet is 23.9±25.5 hours. For the 0.01 mg ethinyl estradiol tablet [light yellow to yellow], the elimination half-life at steady state, Day 28, is 18.9±8.3 hours.

Special Populations

Race

There is no information to determine the effect of race on the pharmacokinetics of VIORELE®.

Hepatic Insufficiency

No formal studies were conducted to evaluate the effect of hepatic disease on the disposition of desogestrel/ethinyl estradiol and ethinyl estradiol.

Renal Insufficiency

No formal studies were conducted to evaluate the effect of renal disease on the disposition of desogestrel/ethinyl estradiol and ethinyl estradiol.

Drug-Drug Interactions

Interactions between desogestrel/ethinyl estradiol and other drugs have been reported in the literature. No formal drug-drug interaction studies were conducted (see PRECAUTIONS section).

INDICATIONS AND USAGE

VIORELE® (desogestrel and ethinyl estradiol tablets, USP and ethinyl estradiol tablets, USP) is indicated for the prevention of pregnancy in women who elect to use this product as a method of contraception.

Oral contraceptives are highly effective. Table II lists the typical accidental pregnancy rates for users of combination oral contraceptives and other methods of contraception. The efficacy of these contraceptive methods, except sterilization, depends upon the reliability with which they are used. Correct and consistent use of these methods can result in lower failure rates.

TABLE II: Percentage of women experiencing an unintended pregnancy during the first year of typical use and the first year of perfect use of contraception and the percentage continuing use at the end of the first year, United States.

 | % of Women Experiencing an Unintended Pregnancy within the First Year of Use |  | % of Women Continuing Use at One Yeara
Method; (1) | Typical Useb; (2) | Perfect Usec; (3) | (4)
Chanced | 85 | 85
Spermicidese | 26 | 6 | 40
Periodic abstinence | 25 |  | 63
Calendar |  | 9
Ovulation Method |  | 3
Sympto-Thermalf |  | 2
Post-Ovulation |  | 1
Withdrawal | 19 | 4
Capg
Parous Women | 40 | 26 | 42
Nulliparous Women | 20 | 9 | 56
Sponge
Parous Women | 40 | 20 | 42
Nulliparous Women | 20 | 9 | 56
Diaphragmg | 20 | 6 | 56
Condomh
Female (Reality) | 21 | 5 | 56
Male | 14 | 3 | 61
Pill | 5 |  | 71
Progestin Only |  | 0.5
Combined |  | 0.1
IUD
Progesterone T | 2 | 1.5 | 81
Copper T 380A | 0.8 | 0.6 | 78
LNg 20 | 0.1 | 0.1 | 81
Depo-Provera | 0.3 | 0.3 | 70
Norplant and Norplant-2 | 0.05 | 0.05 | 88
Female sterilization | 0.5 | 0.5 | 100
Male sterilization | 0.15 | 0.1 | 100
Adapted from Hatcher etal., 1998, Ref#1.

a) Among couples attempting to avoid pregnancy, the percentage who continue to use a method for one year.

b) Among typical couples who initiate use of a method (not necessarily for the first time), the percentage who experience an accidental pregnancy during the first year if they do not stop use for any other reason.

c) Among couples who initiate use of a method (not necessarily for the first time) and who use it perfectly (both consistently and correctly), the percentage who experience an accidental pregnancy during the first year if they do not stop use for any other reason.

d) The percents becoming pregnant in columns (2) and (3) are based on data from populations where contraception is not used and from women who cease using contraception in order to become pregnant. Among such populations, about 89% become pregnant within one year. This estimate was lowered slightly (to 85%) to represent the percent who would become pregnant within one year among women now relying on reversible methods of contraception if they abandoned contraception altogether.

e) Foams, creams, gels, vaginal suppositories, and vaginal film.

f) Cervical mucus (ovulation) method supplemented by calendar in the pre-ovulatory and basal body temperature in the post-ovulatory phases.

g) With spermicidal cream or jelly.

h) Without spermicides.

CONTRAINDICATIONS

Oral contraceptives should not be used in women who currently have the following conditions:

- Thrombophlebitis or thromboembolic disorders
- A past history of deep vein thrombophlebitis or thromboembolic disorders
- Cerebral vascular or coronary artery disease
- Current diagnosis of, or history of, breast cancer, which may be hormone-sensitive
- Undiagnosed abnormal genital bleeding
- Cholestatic jaundice of pregnancy or jaundice with prior pill use
- Hepatic adenomas or carcinomas
- Are receiving Hepatitis C drug combinations containing ombitasvir/paritaprevir/ritonavir, with or without dasabuvir, due to the potential for ALT elevations (see WARNINGS, RISK OF LIVER ENZYME ELEVATIONS WITH CONCOMITANT HEPATITIS C TREATMENT).

WARNINGS

The use of oral contraceptives is associated with increased risks of several serious conditions including myocardial infarction, thromboembolism, stroke, hepatic neoplasia, and gallbladder disease, although the risk of serious morbidity or mortality is very small in healthy women without underlying risk factors. The risk of morbidity and mortality increases significantly in the presence of other underlying risk factors such as hypertension, hyperlipidemias, obesity, and diabetes.

Practitioners prescribing oral contraceptives should be familiar with the following information relating to these risks.

The information contained in this package insert is principally based on studies carried out in patients who used oral contraceptives with formulations of higher doses of estrogens and progestogens than those in common use today. The effect of long-term use of the oral contraceptives with formulations of lower doses of both estrogens and progestogens remains to be determined.

Throughout this labeling, epidemiologic studies reported are of two types: retrospective or case control studies and prospective or cohort studies. Case control studies provide a measure of the relative risk of a disease, namely, a ratio of the incidence of a disease among oral contraceptive users to that among non-users. The relative risk does not provide information on the actual clinical occurrence of a disease. Cohort studies provide a measure of attributable risk, which is the difference in the incidence of disease between oral contraceptive users and non-users. The attributable risk does provide information about the actual occurrence of a disease in the population (Adapted from refs. 2 and 3 with the author’s permission). For further information, the reader is referred to a text on epidemiologic methods.

1. Thromboembolic disorders and other vascular problems

a. Thromboembolism

An increased risk of thromboembolic and thrombotic disease associated with the use of oral contraceptives is well established. Case control studies have found the relative risk of users compared to non-users to be 3 for the first episode of superficial venous thromboembolic disease, 4 to 11 for deep vein thrombosis or pulmonary embolism, and 1.5 to 6 for women with predisposing conditions for venous thromboembolic disease (2,3,19-24). Cohort studies have shown the relative risk to be somewhat lower, about 3 for new cases and about 4.5 for new cases requiring hospitalization (25). The risk of thromboembolic disease associated with oral contraceptives is not related to length of use and disappears after pill use is stopped (2).

Several epidemiologic studies indicate that third generation oral contraceptives, including those containing desogestrel, are associated with a higher risk of venous thromboembolism than certain second generation oral contraceptives (102-104). In general, these studies indicate an approximate two-fold increased risk, which corresponds to an additional 1 to 2 cases of venous thromboembolism per 10,000 women-years of use. However, data from additional studies have not shown this two-fold increase in risk.

A two- to four-fold increase in relative risk of post-operative thromboembolic complications has been reported with the use of oral contraceptives (9, 26). The relative risk of venous thrombosis in women who have predisposing conditions is twice that of women without such medical conditions (9, 26). If feasible, oral contraceptives should be discontinued at least four weeks prior to and for two weeks after elective surgery of a type associated with an increase in risk of thromboembolism and during and following prolonged immobilization. Since the immediate postpartum period is also associated with an increased risk of thromboembolism, oral contraceptives should be started no earlier than four weeks after delivery in women who elect not to breast-feed.

b. Myocardial infarction

An increased risk of myocardial infarction has been attributed to oral contraceptive use. This risk is primarily in smokers or women with other underlying risk factors for coronary artery disease such as hypertension, hypercholesterolemia, morbid obesity, and diabetes. The relative risk of heart attack for current oral contraceptive users has been estimated to be two to six (4-10). The risk is very low in women under the age of 30.

Smoking in combination with oral contraceptive use has been shown to contribute substantially to the incidence of myocardial infarction in women in their mid-thirties or older with smoking accounting for the majority of excess cases (11). Mortality rates associated with circulatory disease have been shown to increase substantially in smokers, over the age of 35 and non-smokers over the age of 40 (Table III) among women who use oral contraceptives.

FIGURE 1: CIRCULATORY DISEASE MORTALITY RATES PER 100,000 WOMAN-YEARS BY AGE, SMOKING STATUS, AND ORAL CONTRACEPTIVE USE

Adapted from P.M. Layde and V. Beral, ref. #12.

Oral contraceptives may compound the effects of well-known risk factors, such as hypertension, diabetes, hyperlipidemias, age and obesity (13). In particular, some progestogens are known to decrease HDL cholesterol and cause glucose intolerance, while estrogens may create a state of hyperinsulinism (14-18). Oral contraceptives have been shown to increase blood pressure among users (see section 10 in WARNINGS). Similar effects on risk factors have been associated with an increased risk of heart disease. Oral contraceptives must be used with caution in women with cardiovascular disease risk factors.

c. Cerebrovascular diseases

Oral contraceptives have been shown to increase both the relative and attributable risks of cerebrovascular events (thrombotic and hemorrhagic strokes), although, in general, the risk is greatest among older (> 35 years), hypertensive women who also smoke. Hypertension was found to be a risk factor for both users and non-users, for both types of strokes, while smoking interacted to increase the risk for hemorrhagic strokes (27-29).

In a large study, the relative risk of thrombotic strokes has been shown to range from 3 for normotensive users to 14 for users with severe hypertension (30). The relative risk of hemorrhagic stroke is reported to be 1.2 for non-smokers who used oral contraceptives, 2.6 for smokers who did not use oral contraceptives, 7.6 for smokers who used oral contraceptives, 1.8 for normotensive users and 25.7 for users with severe hypertension (30). The attributable risk is also greater in older women (3).

d. Dose-related risk of vascular disease from oral contraceptives

A positive association has been observed between the amount of estrogen and progestogen in oral contraceptives and the risk of vascular disease (31-33). A decline in serum high-density lipoproteins (HDL) has been reported with many progestational agents (14-16). A decline in serum high-density lipoproteins has been associated with an increased incidence of ischemic heart disease. Because estrogens increase HDL cholesterol, the net effect of an oral contraceptive depends on a balance achieved between doses of estrogen and progestogen and the nature and absolute amount of progestogens used in the contraceptives. The amount of both hormones should be considered in the choice of an oral contraceptive.

Minimizing exposure to estrogen and progestogen is in keeping with good principles of therapeutics. For any particular estrogen/progestogen combination, the dosage regimen prescribed should be one which contains the least amount of estrogen and progestogen that is compatible with a low failure rate and the needs of the individual patient. New acceptors of oral contraceptive agents should be started on preparations containing 0.035 mg or less of estrogen.

e. Persistence of risk of vascular disease

There are two studies which have shown persistence of risk of vascular disease for ever-users of oral contraceptives. In a study in the United States, the risk of developing myocardial infarction after discontinuing oral contraceptives persists for at least 9 years for women 40 to 49 years old who had used oral contraceptives for five or more years, but this increased risk was not demonstrated in other age groups (8). In another study in Great Britain, the risk of developing cerebrovascular disease persisted for at least 6 years after discontinuation of oral contraceptives, although excess risk was very small (34). However, both studies were performed with oral contraceptive formulations containing 50 micrograms or more of estrogen.

2. Estimates of mortality from contraceptive use

One study gathered data from a variety of sources which have estimated the mortality rate associated with different methods of contraception at different ages (Table IV). These estimates include the combined risk of death associated with contraceptive methods plus the risk attributable to pregnancy in the event of method failure. Each method of contraception has its specific benefits and risks. The study concluded that with the exception of oral contraceptive users 35 and older who smoke and 40 and older who do not smoke, mortality associated with all methods of birth control is low and below that associated with childbirth.

The observation of a possible increase in risk of mortality with age for oral contraceptive users is based on data gathered in the 1970's - but not reported until 1983 (35). However, current clinical practice involves the use of lower estrogen formulations combined with careful consideration of risk factors.

Because of these changes in practice and, also, because of some limited new data which suggest that the risk of cardiovascular disease with the use of oral contraceptives may now be less than previously observed (100,101), the Fertility and Maternal Health Drugs Advisory Committee was asked to review the topic in 1989. The Committee concluded that although cardiovascular disease risks may be increased with oral contraceptive use after age 40 in healthy non-smoking women (even with the newer low-dose formulations), there are also greater potential health risks associated with pregnancy in older women and with the alternative surgical and medical procedures which may be necessary if such women do not have access to effective and acceptable means of contraception.

Therefore, the Committee recommended that the benefits of low-dose oral contraceptive use by healthy non-smoking women over 40 may outweigh the possible risks. Of course, older women, as all women who take oral contraceptives, should take the lowest possible dose formulation that is effective.

TABLE III: ANNUAL NUMBER OF BIRTH-RELATED OR METHOD-RELATED DEATHS ASSOCIATED WITH CONTROL OF FERTILITY PER 100,000 NON-STERILE WOMEN, BY FERTILITY CONTROL METHOD ACCORDING TO AGE
Method of control and outcome | 15 to 19 | 20 to 24 | 25 to 29 | 30 to 34 | 35 to 39 | 40 to 44
No fertility control methodsa | 7 | 7.4 | 9.1 | 14.8 | 25.7 | 28.2
Oral contraceptives non-smokerb | 0.3 | 0.5 | 0.9 | 1.9 | 13.8 | 31.6
Oral contraceptives smokerb | 2.2 | 3.4 | 6.6 | 13.5 | 51.1 | 117.2
IUDb | 0.8 | 0.8 | 1 | 1 | 1.4 | 1.4
Condoma | 1.1 | 1.6 | 0.7 | 0.2 | 0.3 | 0.4
Diaphragm/spermicidea | 1.9 | 1.2 | 1.2 | 1.3 | 2.2 | 2.8
Periodic abstinencea | 2.5 | 1.6 | 1.6 | 1.7 | 2.9 | 3.6
Adapted from H.W. Ory, ref. #35.

a)Deaths are birth related

b)Deaths are method related

3. Malignant Neoplasms

Breast Cancer

VIORELE® is contraindicated in females who currently have or have had breast cancer because breast cancer may be hormonally sensitive (see Contraindications).

Epidemiology studies have not found a consistent association between use of combined oral contraceptives (COCs) and breast cancer risk. Studies do not show an association between ever (current or past) use of COCs and risk of breast cancer. However, some studies report a small increase in the risk of breast cancer among current or recent users (<6 months since last use) and current users with longer duration of COC use (see ADVERSE REACTIONS, Postmarketing Experience).

Cervical Cancer

Some studies suggest that oral contraceptive use has been associated with an increase in the risk of cervical intra-epithelial neoplasia in some populations of women (48). However, there continues to be controversy about the extent to which such findings may be due to differences in sexual behavior and other factors.

4. Hepatic neoplasia

Benign hepatic adenomas are associated with oral contraceptive use, although the incidence of benign tumors is rare in the United States. Indirect calculations have estimated the attributable risk to be in the range of 3.3 cases/100,000 for users, a risk that increases after four or more years of use especially with oral contraceptives of higher dose (49). Rupture of rare, benign, hepatic adenomas may cause death through intra-abdominal hemorrhage (50, 51).

Studies from Britain have shown an increased risk of developing hepatocellular carcinoma (43-45) in long-term (> 8 years) oral contraceptive users. However, these cancers are extremely rare in the US and the attributable risk (the excess incidence) of liver cancers in oral contraceptive users approaches less than one per million users.

5. Risk of Liver Enzyme Elevations with Concomitant Hepatitis C Treatment

During clinical trials with the Hepatitis C combination drug regimen that contains ombitasvir/paritaprevir/ritonavir, with or without dasabuvir, ALT elevations greater than 5 times the upper limit of normal (ULN), including some cases greater than 20 times the ULN, were significantly more frequent in women using ethinyl estradiol-containing medications such as COCs. Discontinue VIORELE® prior to starting therapy with the combination drug regimen ombitasvir/paritaprevir/ritonavir, with or without dasabuvir [see CONTRAINDICATIONS]. VIORELE® can be restarted approximately 2 weeks following completion of treatment with the combination drug regimen.

6. Ocular lesions

There have been clinical case reports of retinal thrombosis associated with the use of oral contraceptives. Oral contraceptives should be discontinued if there is unexplained partial or complete loss of vision; onset of proptosis or diplopia; papilledema; or retinal vascular lesions. Appropriate diagnostic and therapeutic measures should be undertaken immediately.

7. Oral contraceptive use before or during early pregnancy

Extensive epidemiologic studies have revealed no increased risk of birth defects in women who have used oral contraceptives prior to pregnancy (55-57). Studies also do not suggest a teratogenic effect, particularly in so far as cardiac anomalies and limb reduction defects are concerned (55, 56, 58, 59), when oral contraceptives are taken inadvertently during early pregnancy.

The administration of oral contraceptives to induce withdrawal bleeding should not be used as a test for pregnancy. Oral contraceptives should not be used during pregnancy to treat threatened or habitual abortion. It is recommended that for any patient who has missed two consecutive periods, pregnancy should be ruled out before continuing oral contraceptive use. If the patient has not adhered to the prescribed schedule, the possibility of pregnancy should be considered at the first missed period. Oral contraceptive use should be discontinued until pregnancy is ruled out.

8. Gallbladder disease

Earlier studies have reported an increased lifetime relative risk of gallbladder surgery in users of oral contraceptives and estrogens (60, 61). More recent studies, however, have shown that the relative risk of developing gallbladder disease among oral contraceptive users may be minimal (62-64). The recent findings of minimal risk may be related to the use of oral contraceptive formulations containing lower hormonal doses of estrogens and progestogens.

9. Carbohydrate and lipid metabolic effects

Oral contraceptives have been shown to cause a decrease in glucose tolerance in a significant percentage of users (17). Oral contraceptives containing greater than 75 micrograms of estrogens cause hyper-insulinism, while lower doses of estrogen cause less glucose intolerance (65). Progestogens increase insulin secretion and create insulin resistance, this effect varying with different progestational agents (17, 66). However, in the non-diabetic woman, oral contraceptives appear to have no effect on fasting blood glucose (67). Because of these demonstrated effects, prediabetic and diabetic women should be carefully monitored while taking oral contraceptives.

A small proportion of women will have persistent hypertriglyceridemia while on the pill. As discussed earlier (see WARNINGS 1.a. and 1.d.), changes in serum triglycerides and lipoprotein levels have been reported in oral contraceptive

users.

10. Elevated blood pressure

An increase in blood pressure has been reported in women taking oral contraceptives (68) and this increase is more likely in older oral contraceptive users (69) and with continued use (61). Data from the Royal College of General Practitioners (12) and subsequent randomized trials have shown that the incidence of hypertension increases with increasing quantities of progestogens.

Women with a history of hypertension or hypertension-related diseases, or renal disease (70) should be encouraged to use another method of contraception. If women elect to use oral contraceptives, they should be monitored closely and if significant elevation of blood pressure occurs, oral contraceptives should be discontinued. For most women, elevated blood pressure will return to normal after stopping oral contraceptives (69), and there is no difference in the occurrence of hypertension between ever- and never-users (68,70,71).

11. Headache

The onset or exacerbation of migraine or development of headache with a new pattern which is recurrent, persistent, or severe requires discontinuation of oral contraceptives and evaluation of the cause.

12. Bleeding irregularities

Breakthrough bleeding and spotting are sometimes encountered in patients on oral contraceptives, especially during the first three months of use. Non-hormonal causes should be considered and adequate diagnostic measures taken to rule out malignancy or pregnancy in the event of breakthrough bleeding, as in the case of any abnormal vaginal bleeding. If pathology has been excluded, time or a change to another formulation may solve the problem. In the event of amenorrhea, pregnancy should be ruled out.

Some women may encounter post-pill amenorrhea or oligomenorrhea, especially when such a condition was pre-existent.

13. Depression

Carefully observe women with a history of depression and discontinue VIORELE if depression recurs to a serious degree.

14. Hereditary Angioedema

In females with hereditary angioedema, exogenous estrogens may induce or exacerbate symptoms of angioedema.

15. Chloasma

Chloasma may occur with VIORELE use, especially in females with a history of chloasma gravidarum. Advise females with a history of chloasma to avoid exposure to the sun or ultraviolet radiation while using VIORELE.

PRECAUTIONS

1. General

Patients should be counseled that this product does not protect against HIV infection (AIDS) and other sexually transmitted infections.

2. Physical examination and follow up

It is good medical practice for all women to have annual history and physical examinations, including women using oral contraceptives. The physical examination, however, may be deferred until after initiation of oral contraceptives if requested by the woman and judged appropriate by the clinician. The physical examination should include special reference to blood pressure, breasts, abdomen, and pelvic organs, including cervical cytology, and relevant laboratory tests. In case of undiagnosed, persistent or recurrent abnormal vaginal bleeding, appropriate measures should be conducted to rule out malignancy. Women with a strong family history of breast cancer or who have breast nodules should be monitored with particular care.

3. Lipid disorders

Women who are being treated for hyperlipidemias should be followed closely if they elect to use oral contraceptives. Some progestogens may elevate LDL levels and may render the control of hyperlipidemias more difficult.

4. Liver function

If jaundice develops in any woman receiving such drugs, the medication should be discontinued. Steroid hormones may be poorly metabolized in patients with impaired liver function.

5. Fluid retention

Oral contraceptives may cause some degree of fluid retention. They should be prescribed with caution, and only with careful monitoring, in patients with conditions which might be aggravated by fluid retention.

6. Contact lenses

Contact lens wearers who develop visual changes or changes in lens tolerance should be assessed by an ophthalmologist.

7. Drug interactions

Reduced efficacy and increased incidence of breakthrough bleeding and menstrual irregularities have been associated with concomitant use of rifampin. A similar association, though less marked, has been suggested with barbiturates, phenylbutazone, phenytoin sodium, carbamazepine and possibly with griseofulvin, ampicillin, and tetracyclines (72).

Combined hormonal contraceptives have been shown to significantly decrease plasma concentrations of lamotrigine when co-administered, likely due to induction of lamotrigine glucuronidation. This may reduce seizure control; therefore, dosage adjustments of lamotrigine may be necessary.

Concomitant Use with Hepatitis C Virus (HCV) Combination Therapy - Liver Enzyme Elevation

Co-administration of VIORELE® with HCV drug combinations containing ombitasvir/paritaprevir/ritonavir, with or without dasabuvir is contraindicated, due to potential for ALT elevations (see CONTRAINDICATIONS, WARNINGS, RISK OF LIVER ENZYME ELEVATIONS WITH CONCOMITANT HEPATITIS C TREATMENT). Co-administration of VIORELE® and glecaprevir/pibrentasvir is not recommended due to potential for ALT elevations.

Consult the labeling of the concurrently-used drug to obtain further information about interactions with hormonal contraceptives or the potential for enzyme alterations.

8. Interactions with laboratory tests

Certain endocrine and liver function tests and blood components may be affected by oral contraceptives:

a. Increased prothrombin and factors VII, VIII, IX and X; decreased antithrombin 3; increased norepinephrine-induced platelet aggregability.
b. Increased thyroid binding globulin (TBG) leading to increased circulating total thyroid hormone, as measured by protein-bound iodine (PBI), T4 by column or by radioimmunoassay. Free T3 resin uptake is decreased, reflecting the elevated TBG; free T4 concentration is unaltered.
c. Other binding proteins may be elevated in serum.
d. Sex hormone-binding globulins are increased and result in elevated levels of total circulating sex steroids; however, free or biologically active levels either decrease or remain unchanged.
e. High-density lipoprotein cholesterol (HDL-C) and triglycerides may be increased, while low-density lipoprotein cholesterol (LDL-C) and total cholesterol (Total-C) may be decreased or unchanged.
f. Glucose tolerance may be decreased.
g. Serum folate levels may be depressed by oral contraceptive therapy. This may be of clinical significance if a woman becomes pregnant shortly after discontinuing oral contraceptives.

9. Carcinogenesis

See WARNINGS section.

10. Pregnancy

Discontinue VIORELE if pregnancy occurs because there is no reason to use COCs in pregnancy. See WARNINGS section.

11. Lactation

Small amounts of oral contraceptive steroids have been identified in human milk, and a few adverse effects on the child have been reported, including jaundice and breast enlargement. In addition, oral contraceptives given in the postpartum period may interfere with lactation by decreasing the quantity and quality of breast milk. If possible, the nursing mother should be advised not to use oral contraceptives but to use other forms of contraception until she has completely weaned her child.

12. Pediatric use

Safety and efficacy of VIORELE® has been established in women of reproductive age. Safety and efficacy are expected to be the same for post-pubertal adolescents under the age of 16 and for users 16 years and older. Use of this product before menarche is not indicated.

PATIENT COUNSELING INFORMATION

Advise the patient to read the FDA-approved patient labeling (PATIENT PACKAGE INSERT BRIEF SUMMARY and DETAILED PATIENT PACKAGE INSERT).

- Counsel patients that cigarette smoking increases the risk of serious cardiovascular events from COC use, and that women who are over 35 years old and smoke should not use COCs (see BOXED WARNING and CONTRAINDICATIONS).
- Counsel patients that the increased risk of venous thromboembolism compared to nonusers of CHCs is greatest after initially starting a CHC or restarting (following a 4-week or greater interruption in intake) the same or a different CHC (see WARNINGS).
- Counsel patients that this product does not protect against HIV-infection (AIDS) and other sexually transmitted infections.
- Counsel patients to take one tablet daily by mouth at the same time every day. Instruct patients what to do in the event pills are missed (see DOSAGE AND ADMINISTRATION).
- Counsel patients to use a back-up or alternative method of contraception when enzyme inducers are used with COCs (see PRECAUTIONS).
- Counsel patients who are breastfeeding or who desire to breastfeed that COCs may reduce breast milk production. This is less likely to occur if breastfeeding is well established (see PRECAUTIONS).
- Counsel any patient who starts VIORELE postpartum, and who has not yet had a period, to use an additional method of contraception until she has taken a white to off-white tablet for 7 consecutive days (see DOSAGE AND ADMINISTRATION).
- Counsel patients that amenorrhea may occur. Pregnancy should be considered in the event of amenorrhea, and should be ruled out if amenorrhea is associated with symptoms of pregnancy, such as morning sickness or unusual breast tenderness (see WARNINGS).
- Counsel patients with a history of depression that depression may reoccur. Women should contact their healthcare provider if depression occurs (see WARNINGS).

ADVERSE REACTIONS

An increased risk of the following serious adverse reactions has been associated with the use of oral contraceptives (see WARNINGS section):

- Thrombophlebitis and venous thrombosis with or without embolism
- Arterial thromboembolism
- Pulmonary embolism
- Myocardial infarction
- Cerebral hemorrhage
- Cerebral thrombosis
- Hypertension
- Gallbladder disease
- Hepatic adenomas or benign liver tumors

Post Marketing Experience

Five studies that compared breast cancer risk between ever-users (current or past use) of COCs and never-users of COCs reported no association between ever use of COCs and breast cancer risk, with effect estimates ranging from 0.90 to 1.12 (Figure 2). (64 to 68).

Three studies compared breast cancer risk between current or recent COC users (<6 months since last use) and never users of COCs (Figure 2). (64, 67, 69) One of these studies reported no association between breast cancer risk and COC use. The other two studies found an increased relative risk of 1.19 to 1.33 with current or recent use. Both of these studies found an increased risk of breast cancer with current use of longer duration, with relative risks ranging from 1.03 with less than one year of COC use to approximately 1.4 with more than 8 to 10 years of COC use.

FIGURE 2: RELEVANT STUDIES OF RISK OF BREAST CANCER WITH COMBINED

ORAL CONTRACEPTIVES

RR = relative risk; OR = odds ratio; HR = hazard ratio. “ever COC” are females with current or past COC use; “never COC use” are females that never used COCs.

There is evidence of an association between the following conditions and the use of oral contraceptives:

- Mesenteric thrombosis
- Retinal thrombosis

The following adverse reactions have been reported in patients receiving oral contraceptives and are believed to be drug-related:

- Nausea
- Vomiting
- Gastrointestinal symptoms (such as abdominal cramps and bloating)
- Breakthrough bleeding
- Spotting
- Change in menstrual flow
- Amenorrhea
- Temporary infertility after discontinuation of treatment
- Edema
- Melasma which may persist
- Breast changes: tenderness, enlargement, secretion
- Change in weight (increase or decrease)
- Change in cervical erosion and secretion
- Diminution in lactation when given immediately postpartum
- Cholestatic jaundice
- Migraine
- Rash (allergic)
- Mental depression
- Reduced tolerance to carbohydrates
- Vaginal candidiasis
- Change in corneal curvature (steepening)
- Intolerance to contact lenses

The following adverse reactions have been reported in users of oral contraceptives and the association has been neither confirmed nor refuted:

- Pre-menstrual syndrome
- Cataracts
- Changes in appetite
- Cystitis-like syndrome
- Headache
- Nervousness
- Dizziness
- Hirsutism
- Loss of scalp hair
- Erythema multiforme
- Erythema nodosum
- Hemorrhagic eruption
- Vaginitis
- Porphyria
- Impaired renal function
- Hemolytic uremic syndrome
- Acne
- Changes in libido
- Colitis
- Budd-Chiari Syndrome

OVERDOSAGE

Serious ill effects have not been reported following acute ingestion of large doses of oral contraceptives by young children. Overdosage may cause nausea, and withdrawal bleeding may occur in females.

NON-CONTRACEPTIVE HEALTH BENEFITS

The following non-contraceptive health benefits related to the use of oral contraceptives are supported by epidemiologic studies which largely utilized oral contraceptive formulations containing estrogen doses exceeding 0.035 mg of ethinyl estradiol or 0.05 mg of mestranol (73-78).

Effects on menses:

- increased menstrual cycle regularity
- decreased blood loss and decreased incidence of iron deficiency anemia
- decreased incidence of dysmenorrhea

Effects related to inhibition of ovulation:

- decreased incidence of functional ovarian cysts
- decreased incidence of ectopic pregnancies

Effects from long-term use:

- decreased incidence of fibroadenomas and fibrocystic disease of the breast
- decreased incidence of acute pelvic inflammatory disease
- decreased incidence of endometrial cancer
- decreased incidence of ovarian cancer

DOSAGE AND ADMINISTRATION

To achieve maximum contraceptive effectiveness, VIORELE® (desogestrel and ethinyl estradiol tablets, USP and ethinyl estradiol tablets, USP) must be taken exactly as directed and at intervals not exceeding 24 hours. VIORELE® may be initiated using either a Sunday start or a Day 1 start.

NOTE: Each cycle pack blister is preprinted with the days of the week, starting with Sunday, to facilitate a Sunday start regimen. Six different “day label strips” are provided with each cycle pack blister in order to accommodate a Day 1 start regimen. In this case, the patient should place the self-adhesive “day label strip” that corresponds to her starting day over the preprinted days.

IMPORTANT: The possibility of ovulation and conception prior to initiation of use of VIORELE® should be considered.

The use of VIORELE® for contraception may be initiated 4 weeks postpartum in women who elect not to breast-feed. When the tablets are administered during the postpartum period, the increased risk of thromboembolic disease associated with the postpartum period must be considered (see CONTRAINDICATIONS and WARNINGS concerning thromboembolic disease. See also PRECAUTIONS for Nursing mothers).

If the patient starts on VIORELE® postpartum, and has not yet had a period, she should be instructed to use another method of contraception until a white to off-white tablet has been taken daily for 7 days.

SUNDAY START

When initiating a Sunday start regimen, another method of contraception should be used until after the first 7 consecutive days of administration.

Using a Sunday start, tablets are taken daily without interruption as follows: The first white to off-white tablet should be taken on the first Sunday after menstruation begins (if menstruation begins on Sunday, the first white to off-white tablet is taken on that day). One white to off-white tablet is taken daily for 21 days, followed by 1 pale green to yellowish green (inert) tablet daily for 2 days and 1 light yellow to yellow (active) tablet daily for 5 days. For all subsequent cycles, the patient then begins a new 28-tablet regimen on the next day (Sunday) after taking the last light yellow to yellow tablet. [If switching from a Sunday start oral contraceptive, the first VIORELE® tablet should be taken on the second Sunday after the last tablet of a 21-day regimen or should be taken on the first Sunday after the last inactive tablet of a 28 day regimen.]

If a patient misses 1 white to off-white tablet, she should take the missed tablet as soon as she remembers. If the patient misses 2 consecutive white to off-white tablets in Week 1 or Week 2, the patient should take 2 tablets the day she remembers and 2 tablets the next day; thereafter, the patient should resume taking 1 tablet daily until she finishes the cycle pack. The patient should be instructed to use a back-up method of birth control if she has intercourse in the 7 days after missing pills. If the patient misses 2 consecutive white to off-white tablets in the third week or misses 3 or more white to off-white tablets in a row at any time during the cycle, the patient should keep taking 1 white to off-white tablet daily until the next Sunday. On Sunday the patient should throw out the rest of that cycle pack and start a new cycle pack that same day. The patient should be instructed to use a back-up method of birth control if she has intercourse in the 7 days after missing pills.

DAY 1 START

Counting the first day of menstruation as “Day 1”, tablets are taken without interruption as follows: One white to off-white tablet daily for 21 days, one pale green to yellowish green (inert) tablet daily for 2 days followed by 1 light yellow to yellow (ethinyl estradiol) tablet daily for 5 days. For all subsequent cycles, the patient then begins a new 28-tablet regimen on the next day after taking the last light yellow to yellow tablet. [If switching directly from another oral contraceptive, the first white to off-white tablet should be taken on the first day of menstruation which begins after the last ACTIVE tablet of the previous product.]

If a patient misses 1 white to off-white tablet, she should take the missed tablet as soon as she remembers. If the patient misses 2 consecutive white to off-white tablets in Week 1 or Week 2, the patient should take 2 tablets the day she remembers and 2 tablets the next day; thereafter, the patient should resume taking 1 tablet daily until she finishes the cycle pack. The patient should be instructed to use a back-up method of birth control if she has intercourse in the 7 days after missing pills. If the patient misses 2 consecutive white to off-white tablets in the third week or if the patient misses 3 or more white to off-white tablets in a row at any time during the cycle, the patient should throw out the rest of that cycle pack and start a new cycle pack that same day. The patient should be instructed to use a back-up method of birth control if she has intercourse in the 7 days after missing pills.

ALL ORAL CONTRACEPTIVES

Breakthrough bleeding, spotting, and amenorrhea are frequent reasons for patients discontinuing oral contraceptives. In breakthrough bleeding, as in all cases of irregular bleeding from the vagina, non-functional causes should be borne in mind. In undiagnosed persistent or recurrent abnormal bleeding from the vagina, adequate diagnostic measures are indicated to rule out pregnancy or malignancy. If both pregnancy and pathology have been excluded, time or a change to another preparation may solve the problem. Changing to an oral contraceptive with a higher estrogen content, while potentially useful in minimizing menstrual irregularity, should be done only if necessary since this may increase the risk of thromboembolic disease.

Use of oral contraceptives in the event of a missed menstrual period:

1. If the patient has not adhered to the prescribed schedule, the possibility of pregnancy should be considered at the time of the first missed period and oral contraceptive use should be discontinued until pregnancy is ruled out.
2. If the patient has adhered to the prescribed regimen and misses two consecutive periods, pregnancy should be ruled out before continuing oral contraceptive use.

HOW SUPPLIED

VIORELE® (desogestrel and ethinyl estradiol tablets, USP and ethinyl estradiol tablets, USP) contains 21 round white to off-white tablets, 2 round pale green to yellowish green tablets and 5 round light yellow to yellow tablets in a blister. Each white to off-white, biconvex, film-coated tablet (debossed with ‘C1’ on one side and ‘G’ on the other side) contains 0.15 mg desogestrel, USP and 0.02 mg ethinyl estradiol, USP. Each pale green to yellowish green, biconvex, film-coated tablet (debossed with ‘C3’ on one side and ‘G’ on the other side) contains inert ingredients. Each light yellow to yellow colored, biconvex, film-coated tablet (debossed with ‘C2’ on one side and ‘G’ on the other side) contains 0.01 mg ethinyl estradiol, USP.

VIORELE® (desogestrel and ethinyl estradiol tablets, USP and ethinyl estradiol tablets, USP) are available in cartons (NDC 68462-318-29) of 3 blisters (NDC 68462-318-84) each containing 28 tablets.

Store at 20°C to 25°C (68°F to 77°F) [see USP Controlled Room Temperature].

REFERENCES

1. Hatcher RA, Trussell J, Stewart F et al. Contraceptive Technology: Seventeenth Revised Edition, New York: Irvington Publishers, 1998, in press.

2. Stadel BV. Oral contraceptives and cardiovascular disease. (Pt. 1). N Engl J Med 1981; 305:612-618.

3. Stadel BV. Oral contraceptives and cardiovascular disease. (Pt. 2). N Engl J Med 1981; 305:672-677.

4. Adam SA, Thorogood M. Oral contraception and myocardial infarction revisited: the effects of new preparations and prescribing patterns. Br J Obstet and Gynecol 1981; 88:838-845.

5. Mann JI, Inman WH. Oral contraceptives and death from myocardial infarction. Br Med J 1975; 2(5965):245-248.

6. Mann JI, Vessey MP, Thorogood M, Doll R. Myocardial infarction in young women with special reference to oral contraceptive practice. Br Med J 1975; 2(5956):241-245.

7. Royal College of General Practitioners' Oral Contraception Study: Further analyses of mortality in oral contraceptive users. Lancet 1981; 1:541-546.

8. Slone D, Shapiro S, Kaufman DW, Rosenberg L, Miettinen OS, Stolley PD. Risk of myocardial infarction in relation to current and discontinued use of oral contraceptives. N Engl J Med 1981; 305:420-424.

9. Vessey MP. Female hormones and vascular disease-an epidemiological overview. Br J Fam Plann 1980; 6:1-12.

10. Russell-Briefel RG, Ezzati TM, Fulwood R, Perlman JA, Murphy RS. Cardiovascular risk status and oral contraceptive use, United States, 1976-80. Prevent Med 1986; 15:352-362.

11. Goldbaum GM, Kendrick JS, Hogelin GC, Gentry EM. The relative impact of smoking and oral contraceptive use on women in the United States. JAMA 1987; 258:1339-1342.

12. Layde PM, Beral V. Further analyses of mortality in oral contraceptive users: Royal College General Practitioners' Oral Contraception Study. (Table 5) Lancet 1981; 1:541-546.

13. Knopp RH. Arteriosclerosis risk: the roles of oral contraceptives and postmenopausal estrogens. J Reprod Med 1986; 31(9) (Supplement):913-921.

14. Krauss RM, Roy S, Mishell DR, Casagrande J, Pike MC. Effects of two low-dose oral contraceptives on serum lipids and lipoproteins: Differential changes in high-density lipoproteins subclasses. Am J Obstet 1983; 145:446-452.

15. Wahl P, Walden C, Knopp R, Hoover J, Wallace R, Heiss G, Rifkind B. Effect of estrogen/progestin potency on lipid/lipoprotein cholesterol. N Engl J Med 1983; 308:862-867.

16. Wynn V, Niththyananthan R. The effect of progestin in combined oral contraceptives on serum lipids with special reference to high-density lipoproteins. Am J Obstet Gynecol 1982; 142:766-771.

17. Wynn V, Godsland I. Effects of oral contraceptives and carbohydrate metabolism. J Reprod Med 1986; 31 (9) (Supplement):892-897.

18. LaRosa JC. Atherosclerotic risk factors in cardiovascular disease. J Reprod Med 1986; 31 (9) (Supplement):906-912.

19. Inman WH, Vessey MP. Investigation of death from pulmonary, coronary, and cerebral thrombosis and embolism in women of child-bearing age. Br Med J 1968; 2 (5599):193-199.

20. Maguire MG, Tonascia J, Sartwell PE, Stolley PD, Tockman MS. Increased risk of thrombosis due to oral contraceptives: a further report. Am J Epidemiol 1979; 110 (2):188-195.

21. Pettiti DB, Wingerd J, Pellegrin F, Ramacharan S. Risk of vascular disease in women: smoking, oral contraceptives, noncontraceptive estrogens, and other factors. JAMA 1979; 242:1150-1154.

22. Vessey MP, Doll R. Investigation of relation between use of oral contraceptives and thromboembolic disease. Br Med J 1968; 2 (5599):199-205.

23. Vessey MP, Doll R. Investigation of relation between use of oral contraceptives and thromboembolic disease. A further report. Br Med J 1969; 2 (5658):651-657.

24. Porter JB, Hunter JR, Danielson DA, Jick H, Stergachis A. Oral contraceptives and non-fatal vascular disease-recent experience. Obstet Gynecol 1982; 59 (3):299-302.

25. Vessey M, Doll R, Peto R, Johnson B, Wiggins P. A long-term follow-up study of women using different methods of contraception: an interim report. Biosocial Sci 1976; 8:375-427.

26. Royal College of General Practitioners: Oral contraceptives, venous thrombosis, and varicose veins. J Royal Coll Gen Pract 1978; 28:393-399.

27. Collaborative Group for the Study of Stroke in Young Women: Oral contraception and increased risk of cerebral ischemia or thrombosis. N Engl J Med 1973; 288:871-878.

28. Petitti DB, Wingerd J. Use of oral contraceptives, cigarette smoking, and risk of subarachnoid hemorrhage. Lancet 1978; 2:234-236.

29. Inman WH. Oral contraceptives and fatal sub-arachnoid hemorrhage. Br Med J 1979; 2 (6203):1468-70.

30. Collaborative Group for the Study of Stroke in Young Women: Oral contraceptives and stroke in young women: associated risk factors. JAMA 1975; 231:718-722.

31. Inman WH, Vessey MP, Westerholm B, Engelund A. Thromboembolic disease and the steroidal content of oral contraceptives. A report to the Committee on Safety of Drugs. Br Med J 1970; 2:203-209.

32. Meade TW, Greenberg G, Thompson SG. Progestogens and cardiovascular reactions associated with oral contraceptives and a comparison of the safety of 50- and 35-mcg oestrogen preparations. Br Med J 1980; 280 (6224):1157-1161.

33. Kay CR. Progestogens and arterial disease-evidence from the Royal College of General Practitioners' Study. Am J Obstet Gynecol 1982; 142:762-765.

34. Royal College of General Practitioners: Incidence of arterial disease among oral contraceptive users. J Royal Coll Gen Pract 1983; 33:75-82.

35. Ory HW. Mortality associated with fertility and fertility control: 1983. Family Planning Perspectives 1983; 15:50-56.

36. The Cancer and Steroid Hormone Study of the Centers for Disease Control and the National Institute of Child Health and Human Development: Oral-contraceptive use and the risk of breast cancer. N Engl J Med 1986; 315:405-411.

37. Pike MC, Henderson BE, Krailo MD, Duke A, Roy S. Breast cancer risk in young women and use of oral contraceptives: possible modifying effect of formulation and age at use. Lancet 1983; 2:926-929.

38. Paul C, Skegg DG, Spears GFS, Kaldor JM. Oral contraceptives and breast cancer: A national study. Br Med J 1986; 293:723-725.

39. Miller DR, Rosenberg L, Kaufman DW, Schottenfeld D, Stolley PD, Shapiro S. Breast cancer risk in relation to early oral contraceptive use. Obstet Gynecol 1986; 68:863-868.

40. Olson H, Olson KL, Moller TR, Ranstam J, Holm P. Oral contraceptive use and breast cancer in young women in Sweden (letter). Lancet 1985; 2:748-749.

41. McPherson K, Vessey M, Neil A, Doll R, Jones L, Roberts M. Early contraceptive use and breast cancer: Results of another case-control study. Br J Cancer 1987; 56:653-660.

42. Huggins GR, Zucker PF. Oral contraceptives and neoplasia: 1987 update. Fertil Steril 1987; 47:733-761.

43. McPherson K, Drife JO. The pill and breast cancer: why the uncertainty? Br Med J 1986; 293:709-710.

44. Shapiro S. Oral contraceptives-time to take stock. N Engl J Med 1987; 315:450-451.

45. Ory H, Naib Z, Conger SB, Hatcher RA, Tyler CW. Contraceptive choice and prevalence of cervical dysplasia and carcinoma in situ. Am J Obstet Gynecol 1976; 124:573-577.

46. Vessey MP, Lawless M, McPherson K, Yeates D. Neoplasia of the cervix uteri and contraception: a possible adverse effect of the pill. Lancet 1983; 2:930.

47. Brinton LA, Huggins GR, Lehman HF, Malli K, Savitz DA, Trapido E, Rosenthal J, Hoover R. Long-term use of oral contraceptives and risk of invasive cervical cancer. Int J Cancer 1986; 38:339-344.

48. WHO Collaborative Study of Neoplasia and Steroid Contraceptives: Invasive cervical cancer and combined oral contraceptives. Br Med J 1985; 209:961-965.

49. Rooks JB, Ory HW, Ishak KG, Strauss LT, Greenspan JR, Hill AP, Tyler CW. Epidemiology of hepatocellular adenoma: the role of oral contraceptive use. JAMA 1979; 242:644-648.

50. Bein NN, Goldsmith HS. Recurrent massive hemorrhage from benign hepatic tumors secondary to oral contraceptives. Br J Surg 1977; 64:433-435.

51. Klatskin G. Hepatic tumors: possible relationship to use of oral contraceptives. Gastroenterology 1977; 73:386-394.

52. Henderson BE, Preston-Martin S, Edmondson HA, Peters RL, Pike MC. Hepatocellular carcinoma and oral contraceptives. Br J Cancer 1983; 48:437-440.

53. Neuberger J, Forman D, Doll R, Williams R. Oral contraceptives and hepatocellular carcinoma. Br Med J 1986; 292:1355-1357.

54. Forman D, Vincent TJ, Doll R. Cancer of the liver and oral contraceptives. Br Med J 1986; 292:1357-1361.

55. Harlap S, Eldor J. Births following oral contraceptive failures. Obstet Gynecol 1980; 55:447-452.

56. Savolainen E, Saksela E, Saxen L. Teratogenic hazards of oral contraceptives analyzed in a national malformation register. Am J Obstet Gynecol 1981; 140:521-524.

57. Janerich DT, Piper JM, Glebatis DM. Oral contraceptives and birth defects. Am J Epidemiol 1980; 112:73-79.

58. Ferencz C, Matanoski GM, Wilson PD, Rubin JD, Neill CA, Gutberlet R. Maternal hormone therapy and congenital heart disease. Teratology 1980; 21:225-239.

59. Rothman KJ, Fyler DC, Goldbatt A, Kreidberg MB. Exogenous hormones and other drug exposures of children with congenital heart disease. Am J Epidemiol 1979; 109:433-439.

60. Boston Collaborative Drug Surveillance Program: Oral contraceptives and venous thromboembolic disease, surgically confirmed gallbladder disease, and breast tumors. Lancet 1973; 1:1399-1404.

61. Royal College of General Practitioners: Oral contraceptives and health. New York, Pittman, 1974.

62. Layde PM, Vessey MP, Yeates D. Risk of gallbladder disease: a cohort study of young women attending family planning clinics. J Epidemiol Community Health 1982; 36:274-278.

63. Rome Group for the Epidemiology and Prevention of Cholelithiasis (GREPCO): Prevalence of gallstone disease in an Italian adult female population. Am J Epidemiol 1984; 119:796-805.

64. Strom BL, Tamragouri RT, Morse ML, Lazar EL, West SL, Stolley PD, Jones JK. Oral contraceptives and other risk factors for gallbladder disease. Clin Pharmacol Ther 1986; 39:335-341.

65. Wynn V, Adams PW, Godsland IF, Melrose J, Niththyananthan R, Oakley NW, Seedj A. Comparison of effects of different combined oral-contraceptive formulations on carbohydrate and lipid metabolism. Lancet 1979; 1:1045-1049.

66. Wynn V. Effect of progesterone and progestins on carbohydrate metabolism. In Progesterone and Progestin. Edited by Bardin CW, Milgrom E, Mauvis-Jarvis P. New York, Raven Press, 1983 pp. 395-410.

67. Perlman JA, Roussell-Briefel RG, Ezzati TM, Lieberknecht G. Oral glucose tolerance and the potency of oral contraceptive progestogens. J Chronic Dis 1985; 38:857-864.

68. Royal College of General Practitioners' Oral Contraception Study: Effect on hypertension and benign breast disease of progestogen component in combined oral contraceptives. Lancet 1977; 1:624.

69. Fisch IR, Frank J. Oral contraceptives and blood pressure. JAMA 1977; 237:2499-2503.

70. Laragh AJ. Oral contraceptive induced hypertension-nine years later. Am J Obstet Gynecol 1976; 126:141-147.

71. Ramcharan S, Peritz E, Pellegrin FA, Williams WT. Incidence of hypertension in the Walnut Creek Contraceptive Drug Study cohort. In Pharmacology of Steroid Contraceptive Drugs. Garattini S, Berendes HW. Eds. New York, Raven Press, 1977 pp. 277-288. (Monographs of the Mario Negri Institute for Pharmacological Research, Milan).

72. Stockley I. Interactions with oral contraceptives. J Pharm 1976; 216:140-143.

73. The Cancer and Steroid Hormone Study of the Centers for Disease Control and the National Institute of Child Health and Human Development: Oral contraceptive use and the risk of ovarian cancer. JAMA 1983; 249:1596-1599.

74. The Cancer and Steroid Hormone Study of the Centers for Disease Control and the National Institute of Child Health and Human Development: Combination oral contraceptive use and the risk of endometrial cancer. JAMA 1987; 257:796-800.

75. Ory HW. Functional ovarian cysts and oral contraceptives: negative association confirmed surgically. JAMA 1974; 228:68-69.

76. Ory HW, Cole P, Macmahon B, Hoover R. Oral contraceptives and reduced risk of benign breast disease. N Engl J Med 1976; 294:419-422.

77. Ory HW. The noncontraceptive health benefits from oral contraceptive use. Fam Plann Perspect 1982; 14:182-184.

78. Ory HW, Forrest JD, Lincoln R. Making Choices: Evaluating the health risks and benefits of birth control methods. New York, The Alan Guttmacher Institute, 1983; p. 1.

79. Schlesselman J, Stadel BV, Murray P, Lai S. Breast Cancer in relation to early use of oral contraceptives 1988; 259:1828-1833.

80. Hennekens CH, Speizer FE, Lipnick RJ, Rosner B, Bain C, Belanger C, Stampfer MJ, Willett W, Peto R. A case-controlled study of oral contraceptive use and breast cancer. JNCI 1984; 72:39-42.

81. LaVecchia C, Decarli A, Fasoli M, Franceschi S, Gentile A, Negri E, Parazzini F, Tognoni G. Oral contraceptives and cancers of the breast and of the female genital tract. Interim results from a case-control study. Br. J. Cancer 1986; 54:311-317.

82. Meirik O, Lund E, Adami H, Bergstrom R, Christoffersen T, Bergsjo P. Oral contraceptive use in breast cancer in young women. A Joint National Case-control study in Sweden and Norway. Lancet 1986; 11:650-654.

83. Kay CR, Hannaford PC. Breast cancer and the pill-A further report from the Royal College of General Practitioners' oral contraception study. Br. J. Cancer 1988; 58:675-680.

84. Stadel BV, Lai S, Schlesselman JJ, Murray P. Oral contraceptives and premenopausal breast cancer in nulliparous women. Contraception 1988; 38:287-299.

85. Miller DR, Rosenberg L, Kaufman DW, Stolley P, Warshauer ME, Shapiro S. Breast cancer before age 45 and oral contraceptive use: New Findings. Am. J. Epidemiol 1989; 129:269-280.

86. The UK National Case-Control Study Group, Oral contraceptive use and breast cancer risk in young women. Lancet 1989; 1:973-982.

87. Schlesselman JJ. Cancer of the breast and reproductive tract in relation to use of oral contraceptives. Contraception 1989; 40:1-38.

88. Vessey MP, McPherson K, Villard-Mackintosh L, Yeates D. Oral contraceptives and breast cancer: latest findings in a large cohort study. Br. J. Cancer 1989; 59:613-617.

89. Jick SS, Walker AM, Stergachis A, Jick H. Oral contraceptives and breast cancer. Br. J. Cancer 1989; 59:618-621.

90. Godsland, I et al. The effects of different formulations of oral contraceptive agents on lipid and carbohydrate metabolism. N Engl J Med 1990; 323:1375-81.

91. Kloosterboer, HJ et al. Selectivity in progesterone and androgen receptor binding of progestogens used in oral contraception. Contraception, 1988; 38:325-32.

92. Van der Vies, J and de Visser, J. Endocrinological studies with desogestrel. Arzneim. Forsch./Drug Res., 1983; 33(l),2:231-6.

93. Data on file, Organon Inc.

94. Fotherby, K. Oral contraceptives, lipids and cardiovascular diseases. Contraception, 1985; Vol. 31; 4:367-94.

95. Lawrence, DM et al. Reduced sex hormone binding globulin and derived free testosterone levels in women with severe acne. Clinical Endocrinology, 1981; 15:87-91.

96. Cullberg, G et al. Effects of a low-dose desogestrel-ethinyl estradiol combination on hirsutism, androgens and sex hormone binding globulin in women with a polycystic ovary syndrome. Acta Obstet Gynecol Scand, 1985; 64:195-202.

97. Jung-Hoffmann, C and Kuhl, H. Divergent effects of two low-dose oral contraceptives on sex hormone-binding globulin and free testosterone. AJOG, 1987; 156:199-203.

98. Hammond, G et al. Serum steroid binding protein concentrations, distribution of progestogens, and bioavailability of testosterone during treatment with contraceptives containing desogestrel or levonorgestrel. Fertil. Steril., 1984; 42:44-51.

99. Palatsi, R et al. Serum total and unbound testosterone and sex hormone binding globulin (SHBG) in female acne patients treated with two different oral contraceptives. Acta Derm Venereol, 1984; 64:517-23.

100. Porter JB, Hunter J, Jick H et al. Oral contraceptives and nonfatal vascular disease. Obstet Gynecol 1985; 66:1-4.

101. Porter JB, Jick H, Walker AM. Mortality among oral contraceptive users. Obstet Gynecol 1987; 7029-32.

102. Jick H, Jick SS, Gurewich V, Myers MW, Vasilakis C. Risk of idiopathic cardiovascular death and non-fatal venous thromboembolism in women using oral contraceptives with differing progestagen components. Lancet, 1995; 346:1589-93.

103. World Health Organization Collaborative Study of Cardiovascular Disease and Steroid Hormone Contraception. Effect of different progestagens in low oestrogen oral contraceptives on venous thromboembolic disease. Lancet, 1995; 346:1582-88.

104. Spitzer WO, Lewis MA, Heinemann LAJ, Thorogood M, MacRae KD on behalf of Transnational Research Group on Oral Contraceptives and Health of Young Women. Third generation oral contraceptives and risk of venous thromboembolic disorders: An international case-control study. Br Med J, 1996; 312:83-88.

105. Christensen J, Petrenaite V, Atterman J, et al. Oral contraceptives induce lamotrigine metabolism: evidence from a double-blind, placebo-controlled trial. Epilepsia 2007;48(3):484-489.

Distributed by:

Glenmark Pharmaceuticals Inc., USA

Elmwood Park, NJ 07407

Questions? 1 (888) 721-7115

www.glenmarkpharma-us.com

May 2025

PATIENT PACKAGE INSERT BRIEF SUMMARY

VIORELE® (Desogestrel and Ethinyl Estradiol Tablets, USP 0.15 mg/0.02 mg and Ethinyl Estradiol Tablets, USP 0.01 mg)

Cigarette smoking increases the risk of serious cardiovascular side effects from oral contraceptive use. This risk increases with age and with heavy smoking (15 or more cigarettes per day) and is quite marked in women over 35 years of age. Women who use oral contraceptives are strongly advised not to smoke.

This product (like all oral contraceptives) is intended to prevent pregnancy. It does not protect against HIV infection (AIDS) and other sexually transmitted infections.

Oral contraceptives, also known as “birth control pills” or “the pill”, are taken to prevent pregnancy, and when taken correctly, have a failure rate of about 1% per year when used without missing any pills. The typical failure rate of large numbers of pill users is less than 5% per year when women who miss pills are included. For most women, oral contraceptives are also free of serious or unpleasant side effects. However, forgetting to take pills considerably increases the chances of pregnancy.

For the majority of women, oral contraceptives can be taken safely. But there are some women who are at high risk of developing certain serious diseases that can be life-threatening or may cause temporary or permanent disability. The risks associated with taking oral contraceptives increase significantly if you:

- smoke
- have high blood pressure, diabetes, high cholesterol
- have or have had clotting disorders, heart attack, stroke, angina pectoris, cancer of the breast, jaundice, or malignant or benign liver tumors.

Although cardiovascular disease risks may be increased with oral contraceptive use after age 40 in healthy, non-smoking women (even with the newer low-dose formulations), there are also greater potential health risks associated with pregnancy in older women.

You should not take the pill if you suspect you are pregnant or have unexplained vaginal bleeding.

Most side effects of the pill are not serious. The most common such effects are nausea, vomiting, bleeding between menstrual periods, weight gain, breast tenderness, headache, and difficulty wearing contact lenses. These side effects, especially nausea and vomiting, may subside within the first three months of use.

The serious side effects of the pill occur very infrequently, especially if you are in good health and are young. However, you should know that the following medical conditions have been associated with or made worse by the pill:

1. Blood clots in the legs (thrombophlebitis) or lungs (pulmonary embolism), stoppage or rupture of a blood vessel in the brain (stroke), blockage of blood vessels in the heart (heart attack or angina pectoris) or other organs of the body. As mentioned above, smoking increases the risk of heart attacks and strokes, and subsequent serious medical consequences.
2. Liver tumors, which may rupture and cause severe bleeding. A possible but not definite association has been found with the pill and liver cancer. However, liver cancers are extremely rare. The chance of developing liver cancer from using the pill is thus even rarer.
3. High blood pressure, although blood pressure usually returns to normal when the pill is stopped.

The symptoms associated with these serious side effects are discussed in the detailed leaflet given to you with your supply of pills. Notify your doctor or healthcare provider if you notice any unusual physical disturbances while taking the pill. In addition, drugs such as rifampin, as well as some anticonvulsants and some antibiotics may decrease oral contraceptive effectiveness.

There may be slight increases in the risk of breast cancer among current users of hormonal birth control pills with longer duration of use of 8 years or more.

Some studies have found an increase in the incidence of cancer of the cervix in women who use oral contraceptives. However, this finding may be related to factors other than the use of oral contraceptives.

Taking the pill provides some important non-contraceptive benefits. These include less painful menstruation, less menstrual blood loss and anemia, fewer pelvic infections, and fewer cancers of the ovary and the lining of the uterus.

Be sure to discuss any medical condition you may have with your doctor or healthcare provider. Your doctor or healthcare provider will take a medical and family history before prescribing oral contraceptives and will examine you. The physical examination may be delayed to another time if you request it and your doctor or healthcare provider believes that it is a good medical practice to postpone it. You should be reexamined at least once a year while taking oral contraceptives. The detailed patient information leaflet gives you further information which you should read and discuss with your doctor or healthcare provider.

This product (like all oral contraceptives) is intended to prevent pregnancy. It does not protect against transmission of HIV (AIDS) and other sexually transmitted infections such as chlamydia, genital herpes, genital warts, gonorrhea, hepatitis B, and syphilis.

INSTRUCTIONS TO PATIENTS

HOW TO TAKE THE PILL

IMPORTANT POINTS TO REMEMBER

BEFORE YOU START TAKING YOUR PILLS:

1. BE SURE TO READ THESE DIRECTIONS:

Before you start taking your pills.

Anytime you are not sure what to do.

2. THE RIGHT WAY TO TAKE THE PILL IS TO TAKE ONE PILL EVERY DAY AT THE SAME TIME.

If you miss pills you could get pregnant. This includes starting the pack late.

The more pills you miss, the more likely you are to get pregnant.

3. MANY WOMEN HAVE SPOTTING OR LIGHT BLEEDING, OR MAY FEEL SICK TO THEIR STOMACH DURING THE FIRST 1 TO 3 PACKS OF PILLS.

If you feel sick to your stomach, do not stop taking the pill. The problem will usually go away. If it doesn't go away, check with your doctor or healthcare provider.

4. MISSING PILLS CAN ALSO CAUSE SPOTTING OR LIGHT BLEEDING, even when you make up these missed pills.

On the days you take 2 pills to make up for missed pills, you could also feel a little sick to your stomach.

5. IF YOU HAVE VOMITING OR DIARRHEA, for any reason, or IF YOU TAKE SOME MEDICINES, including some antibiotics, your pills may not work as well.

Use a back-up method (such as condoms, foam, or sponge) until you check with your doctor or healthcare provider.

6. IF YOU HAVE TROUBLE REMEMBERING TO TAKE THE PILL, talk to your doctor or healthcare provider about how to make pill-taking easier or about using another method of birth control.

7. IF YOU HAVE ANY QUESTIONS OR ARE UNSURE ABOUT THE INFORMATION IN THIS LEAFLET, call your doctor or healthcare provider.

BEFORE YOU START TAKING YOUR PILLS

1. DECIDE WHAT TIME OF DAY YOU WANT TO TAKE YOUR PILL.

It is important to take it at about the same time every day.

2. LOOK AT YOUR PILL PACK: IT WILL HAVE 28 PILLS:

This 28-pill pack has 26 “active” [white to off-white and light yellow to yellow] pills (with hormones) and 2 “inactive” [pale green to yellowish green] pills (without hormones).

3. ALSO FIND:

1. where on the pack to start taking the pills,
2. in what order to take the pills (follow the arrows) and
3. the week numbers as shown in the picture below.

4. BE SURE YOU HAVE READY AT ALL TIMES:

ANOTHER KIND OF BIRTH CONTROL (such as condoms, foam, or sponge) to use as a back-up in case you miss pills.

AN EXTRA, FULL PILL PACK.

WHEN TO START THE FIRST PACK OF PILLS

You have a choice of which day to start taking your first pack of pills. Decide with your doctor or healthcare provider which is the best day for you. Pick a time of day which will be easy to remember.

DAY 1 START:

1. Pick the day label strip that starts with the first day of your period (this is the day you start bleeding or spotting, even if it is almost midnight when the bleeding begins).

2. Place this day label strip in the cycle tablet blister over the area that has the days of the week (starting with Sunday) imprinted.

Note: If the first day of your period is a Sunday, you can skip steps #1 and #2.

3. Take the first “active” [white to off-white] pill of the first pack during the first 24 hours of your period.

4. You will not need to use a back-up method of birth control, since you are starting the pill at the beginning of your period.

SUNDAY START:

1. Take the first “active” [white to off-white] pill of the first pack on the Sunday after your period starts, even if you are still bleeding. If your period begins on Sunday, start the pack that same day.
2. Use another method of birth control as a back-up method if you have sex anytime from the Sunday you start your first pack until the next Sunday (7 days). Condoms, foam, or the sponge are good back-up methods of birth control.

WHAT TO DO DURING THE MONTH

1. TAKE ONE PILL AT THE SAME TIME EVERY DAY UNTIL THE PACK IS EMPTY.

Do not skip pills even if you are spotting or bleeding between monthly periods or feel sick to your stomach (nausea).

Do not skip pills even if you do not have sex very often.

2. WHEN YOU FINISH A PACK OR SWITCH YOUR BRAND OF PILLS:

21 pills: Wait 7 days to start the next pack. You will probably have your period during that week. Be sure that no more than 7 days pass between 21-day packs.

28 pills: Start the next pack on the day after your last pill. Do not wait any days between packs.

WHAT TO DO IF YOU MISS PILLS

If you MISS 1 “active” [white to off-white] pill:

1. Take it as soon as you remember. Take the next pill at your regular time. This means you take 2 pills in 1 day.
2. You do not need to use a back-up birth control method if you have sex.

If you MISS 2 “active” [white to off-white] pills in a row in WEEK 1 OR WEEK 2 of your pack:

1. Take 2 pills on the day you remember and 2 pills the next day.
2. Then take 1 pill a day until you finish the pack.
3. You MAY BECOME PREGNANT if you have sex in the 7 days after you miss pills.

You MUST use another birth control method (such as condoms, foam, or sponge) as a back-up method for those 7 days.

If you MISS 2 “active” [white to off-white] pills in a row in WEEK 3:

1. If you are a Day 1 Starter:

THROW OUT the rest of the pill pack and start a new pack that same day.

If you are a Sunday Starter:

Keep taking 1 pill every day until Sunday.

On Sunday, THROW OUT the rest of the pack and start a new pack of pills that same day.

2. You may not have your period this month but this is expected. However, if you miss your period 2 months in a row, call your doctor or healthcare provider because you might be pregnant.

3. You MAY BECOME PREGNANT if you have sex in the 7 days after you miss pills. You MUST use another birth control method (such as condoms, foam, or sponge) as a back-up method for those 7 days.

If you MISS 3 OR MORE “active” [white to off-white] pills in a row (during the first 3 weeks):

1. If you are a Day 1 Starter:

THROW OUT the rest of the pill pack and start a new pack that same day.

If you are a Sunday Starter:

Keep taking 1 pill every day until Sunday.

On Sunday, THROW OUT the rest of the pack and start a new pack of pills that same day.

2. You may not have your period this month but this is expected. However, if you miss your period 2 months in a row, call your doctor or healthcare provider because you might be pregnant.

3. You MAY BECOME PREGNANT if you have sex in the 7 days after you miss pills. You MUST use another birth control method (such as condoms, foam, or sponge) as a back-up method for those 7 days.

A REMINDER FOR THOSE ON 28-DAY PACKS

If you forget any of the 2 [pale green to yellowish green] or 5 [light yellow to yellow] pills in Week 4:

THROW AWAY the pills you missed.

Keep taking 1 pill each day until the pack is empty.

You do not need a back-up method.

FINALLY, IF YOU ARE STILL NOT SURE WHAT TO DO ABOUT THE PILLS YOU HAVE MISSED:

Use a BACK-UP METHOD anytime you have sex.

KEEP TAKING ONE “ACTIVE” [WHITE TO OFF-WHITE] PILL EACH DAY until you can reach your doctor or healthcare provider.

DETAILED PATIENT PACKAGE INSERT

VIORELE® (Desogestrel and Ethinyl Estradiol Tablets, USP 0.15 mg/0.02 mg and Ethinyl Estradiol Tablets, USP 0.01 mg)

This product (like all oral contraceptives) is intended to prevent pregnancy. It does not protect against HIV infection (AIDS) and other sexually transmitted infections.

Rx only

PLEASE NOTE: This labeling is revised from time to time as important new medical information becomes available. Therefore, please review this labeling carefully.

DESCRIPTION

The following oral contraceptive product contains a combination of a progestin and estrogen, the two kinds of female hormones:

Each white to off-white tablet contains 0.15 mg desogestrel, USP and 0.02 mg ethinyl estradiol, USP. Each pale green to yellowish green tablet contains inert ingredients and each light yellow to yellow tablet contains 0.01 mg ethinyl estradiol, USP.

INTRODUCTION

Any woman who considers using oral contraceptives (the birth control pill or the pill) should understand the benefits and risks of using this form of birth control. This leaflet will give you much of the information you will need to make this decision and will also help you determine if you are at risk of developing any of the serious side effects of the pill. It will tell you how to use the pill properly so that it will be as effective as possible. However, this leaflet is not a replacement for a careful discussion between you and your doctor or healthcare provider. You should discuss the information provided in this leaflet with him or her, both when you first start taking the pill and during your revisits. You should also follow your doctor's or healthcare provider's advice with regard to regular check-ups while you are on the pill.

EFFECTIVENESS OF ORAL CONTRACEPTIVES

Oral contraceptives or “birth control pills” or “the pill” are used to prevent pregnancy and are more effective than other non-surgical methods of birth control. When they are taken correctly, the chance of becoming pregnant is less than 1% (1 pregnancy per 100 women per year of use) when used perfectly, without missing any pills. Typical failure rates are actually 5% per year. The chance of becoming pregnant increases with each missed pill during a menstrual cycle.

In comparison, typical failure rates for other methods of birth control during the first year of use are as follows:

Implants (2 or 6 capsules): <1% | Male sterilization: <1%
Injection: <1% | Cervical Cap with spermicides: 20 to 40%
IUD: < 1 to 2% | Condom alone (male): 14%
Diaphragm with spermicides: 20% | Condom alone (female): 21%
Spermicides alone: 26% | Periodic abstinence: 25%
Vaginal sponge: 20 to 40% | Withdrawal: 19%
Female sterilization: <1% | No methods: 85%.

WHO SHOULD NOT TAKE ORAL CONTRACEPTIVES

Cigarette smoking increases the risk of serious cardiovascular side effects from oral contraceptive use. This risk increases with age and with heavy smoking (15 or more cigarettes per day) and is quite marked in women over 35 years of age. Women who use oral contraceptives are strongly advised not to smoke.

Some women should not use the pill. For example, you should not take the pill if you are pregnant or think you may be pregnant. You should also not use the pill if you have any of the following conditions:

- A history of heart attack or stroke
- Blood clots in the legs (thrombophlebitis), lungs (pulmonary embolism), or eyes
- A history of blood clots in the deep veins of your legs
- Chest pain (angina pectoris)
- Known or suspected breast cancer
- Unexplained vaginal bleeding (until a diagnosis is reached by your doctor)
- Yellowing of the whites of the eyes or of the skin (jaundice) during pregnancy or during previous use of the pill
- Liver tumor (benign or cancerous)
- Hepatitis C and are taking any drug combination containing ombitasvir/paritaprevir/ritonavir, with or without dasabuvir. This may increase levels of the liver enzyme "alanine aminotransferase" (ALT) in the blood.

Tell your doctor or healthcare provider if you have ever had any of these conditions. Your doctor or healthcare provider can recommend another method of birth control.

OTHER CONSIDERATIONS BEFORE TAKING ORAL CONTRACEPTIVES

Tell your doctor or healthcare provider if you have:

- Breast nodules, fibrocystic disease of the breast, an abnormal breast x-ray or mammogram
- Diabetes
- Elevated cholesterol or triglycerides
- High blood pressure
- Migraine or other headaches or epilepsy
- Depression
- Gallbladder, heart, or kidney disease
- History of scanty or irregular menstrual periods.

Women with any of these conditions should be checked often by their doctor or healthcare provider if they choose to use oral contraceptives.

Also, be sure to inform your doctor or healthcare provider if you smoke or are on any medications.

RISKS OF TAKING ORAL CONTRACEPTIVES

1. Risk of developing blood clots

Blood clots and blockage of blood vessels are one of the most serious side effects of taking oral contraceptives and can cause death or serious disability. In particular, a clot in the leg can cause thrombophlebitis and a clot that travels to the lungs can cause a sudden blockage of the vessel carrying blood to the lungs. The risks of these side effects may be greater with desogestrel-containing oral contraceptives such as desogestrel/ethinyl estradiol and ethinyl estradiol than with certain other low-dose pills. Rarely, clots occur in the blood vessels of the eye and may cause blindness, double vision, or impaired vision.

If you take oral contraceptives and need elective surgery, need to stay in bed for a prolonged illness or have recently delivered a baby, you may be at risk of developing blood clots. You should consult your doctor or healthcare provider about stopping oral contraceptives three to four weeks before surgery and not taking oral contraceptives for two weeks after surgery or during bed rest. You should also not take oral contraceptives soon after delivery of a baby. It is advisable to wait for at least four weeks after delivery if you are not breastfeeding or four weeks after a second trimester abortion. If you are breastfeeding, you should wait until you have weaned your child before using the pill (see Breastfeeding in GENERAL PRECAUTIONS).

The risk of circulatory disease in oral contraceptive users may be higher in users of high dose pills and may be greater with longer duration of oral contraceptive use. In addition, some of these increased risks may continue for a number of years after stopping oral contraceptives. The risk of venous thromboembolic disease associated with oral contraceptives does not increase with length of use and disappears after pill use is stopped. The risk of abnormal blood clotting increases with age in both users and non-users of oral contraceptives, but the increased risk from the oral contraceptive appears to be present at all ages. For women aged 20 to 44 it is estimated that about 1 in 2000 using oral contraceptives will be hospitalized each year because of abnormal clotting. Among non-users in the same age group, about 1 in 20,000 would be hospitalized each year. For oral contraceptive users in general, it has been estimated that in women between the ages of 15 and 34 the risk of death due to a circulatory disorder is about 1 in 12,000 per year, whereas for non-users the rate is about 1 in 50,000 per year. In the age group 35 to 44, the risk is estimated to be about 1 in 2500 per year for oral contraceptive users and about 1 in 10,000 per year for non-users.

2. Heart attacks and strokes

Oral contraceptives may increase the tendency to develop strokes (stoppage or rupture of blood vessels in the brain) and angina pectoris and heart attacks (blockage of blood vessels in the heart). Any of these conditions can cause death or serious disability.

Smoking greatly increases the possibility of suffering heart attacks and strokes. Furthermore, smoking and the use of oral contraceptives greatly increase the chances of developing and dying of heart disease.

3. Gallbladder disease

Oral contraceptive users probably have a greater risk than non-users of having gallbladder disease, although this risk may be related to pills containing high doses of estrogens.

4. Liver tumors

In rare cases, oral contraceptives can cause benign but dangerous liver tumors. These benign liver tumors can rupture and cause fatal internal bleeding. In addition, a possible but not definite association has been found with the pill and liver cancers in two studies, in which a few women who developed these very rare cancers were found to have used oral contraceptives for long periods. However, liver cancers are extremely rare. The chance of developing liver cancer from using the pill is thus even rarer.

5. Risk of Cancer

It is not known if hormonal birth control pills cause breast cancer. Some studies, but not all, suggest that there could be a slight increase in the risk of breast cancer among current users with longer duration of use.

If you have breast cancer now, or have had it in the past, do not use hormonal birth control because some breast cancers are sensitive to hormones.

Some studies have found an increase in the incidence of cancer of the cervix in women who use oral contraceptives. However, this finding may be related to factors other than the use of oral contraceptives. There is insufficient evidence to rule out the possibility that pills may cause such cancers.

ESTIMATED RISK OF DEATH FROM A BIRTH CONTROL METHOD OR PREGNANCY

All methods of birth control and pregnancy are associated with a risk of developing certain diseases which may lead to disability or death. An estimate of the number of deaths associated with different methods of birth control and pregnancy has been calculated and is shown in the following table.

ANNUAL NUMBER OF BIRTH-RELATED OR METHOD-RELATED DEATHS ASSOCIATED WITH CONTROL OF FERTILITY PER 100,000 NON-STERILE WOMEN, BY FERTILITY CONTROL METHOD ACCORDING TO AGE
Method of control and outcome | 15 to 19 | 20 to 24 | 25 to 29 | 30 to 34 | 35 to 39 | 40 to 44
No fertility control methods* | 7 | 7.4 | 9.1 | 14.8 | 25.7 | 28.2
Oral contraceptives non-smoker** | 0.3 | 0.5 | 0.9 | 1.9 | 13.8 | 31.6
Oral contraceptives smoker** | 2.2 | 3.4 | 6.6 | 13.5 | 51.1 | 117.2
IUD** | 0.8 | 0.8 | 1 | 1 | 1.4 | 1.4
Condom* | 1.1 | 1.6 | 0.7 | 0.2 | 0.3 | 0.4
Diaphragm/spermicide* | 1.9 | 1.2 | 1.2 | 1.3 | 2.2 | 2.8
Periodic abstinence* | 2.5 | 1.6 | 1.6 | 1.7 | 2.9 | 3.6

* Deaths are birth related

** Deaths are method related

In the above table, the risk of death from any birth control method is less than the risk of childbirth, except for oral contraceptive users over the age of 35 who smoke and pill users over the age of 40 even if they do not smoke. It can be seen in the table that for women aged 15 to 39, the risk of death was highest with pregnancy (7 to 26 deaths per 100,000 women, depending on age). Among pill users who do not smoke, the risk of death is always lower than that associated with pregnancy for any age group, although over the age of 40, the risk increases to 32 deaths per 100,000 women, compared to 28 associated with pregnancy at that age. However, for pill users who smoke and are over the age of 35, the estimated number of deaths exceeds those for other methods of birth control. If a woman is over the age of 40 and smokes, her estimated risk of death is four times higher (117/100,000 women) than the estimated risk associated with pregnancy (28/100,000 women) in that age group.

The suggestion that women over 40 who do not smoke should not take oral contraceptives is based on information from older, high-dose pills and on less selective use of pills than is practiced today. An Advisory Committee of the FDA discussed this issue in 1989 and recommended that the benefits of oral contraceptive use by healthy, non-smoking women over 40 years of age may outweigh the possible risks. However, all women, especially older women, are cautioned to use the lowest dose pill that is effective.

WARNING SIGNALS

If any of these adverse effects occur while you are taking oral contraceptives, call your doctor or healthcare provider immediately:

- Sharp chest pain, coughing of blood, or sudden shortness of breath (indicating a possible clot in the lung)
- Pain in the calf (indicating a possible clot in the leg)
- Crushing chest pain or heaviness in the chest (indicating a possible heart attack)
- Sudden severe headache or vomiting, dizziness or fainting, disturbances of vision or speech, weakness, or numbness in an arm or leg (indicating a possible stroke)
- Sudden partial or complete loss of vision (indicating a possible clot in the eye)
- Breast lumps (indicating possible breast cancer or fibrocystic disease of the breast; ask your doctor or healthcare provider to show you how to examine your breasts)
- Severe pain or tenderness in the stomach area (indicating a possibly ruptured liver tumor)
- Difficulty in sleeping, weakness, lack of energy, fatigue, or change in mood (possibly indicating severe depression)
- Jaundice or a yellowing of the skin or eyeballs, accompanied frequently by fever, fatigue, loss of appetite, dark colored urine, or light colored bowel movements (indicating possible liver problems).

SIDE EFFECTS OF ORAL CONTRACEPTIVES

1. Vaginal bleeding

Irregular vaginal bleeding or spotting may occur while you are taking the pills. Irregular bleeding may vary from slight staining between menstrual periods to breakthrough bleeding which is a flow much like a regular period. Irregular bleeding occurs most often during the first few months of oral contraceptive use, but may also occur after you have been taking the pill for some time. Such bleeding may be temporary and usually does not indicate any serious problems. It is important to continue taking your pills on schedule. If the bleeding occurs in more than one cycle or lasts for more than a few days, talk to your doctor or healthcare provider.

2. Contact lenses

If you wear contact lenses and notice a change in vision or an inability to wear your lenses, contact your doctor or healthcare provider.

3. Fluid retention

Oral contraceptives may cause edema (fluid retention) with swelling of the fingers or ankles and may raise your blood pressure. If you experience fluid retention, contact your doctor or healthcare provider.

4. Melasma

A spotty darkening of the skin is possible, particularly of the face.

5. Other side effects

Other side effects may include nausea and vomiting, change in appetite, headache, nervousness, depression, dizziness, loss of scalp hair, rash, and vaginal infections.

If any of these side effects bother you, call your doctor or healthcare provider.

GENERAL PRECAUTIONS

1. Missed periods and use of oral contraceptives before or during early pregnancy

There may be times when you may not menstruate regularly after you have completed taking a cycle of pills. If you have taken your pills regularly and miss one menstrual period, continue taking your pills for the next cycle but be sure to inform your doctor or healthcare provider before doing so. If you have not taken the pills daily as instructed and missed a menstrual period, or if you missed two consecutive menstrual periods, you may be pregnant. Check with your doctor or healthcare provider immediately to determine whether you are pregnant. Do not continue to take oral contraceptives until you are sure you are not pregnant, but continue to use another method of contraception.

There is no conclusive evidence that oral contraceptive use is associated with an increase in birth defects, when taken inadvertently during early pregnancy. Previously, a few studies had reported that oral contraceptives might be associated with birth defects, but these studies have not been confirmed. Nevertheless, oral contraceptives or any other drugs should not be used during pregnancy unless clearly necessary and prescribed by your doctor or healthcare provider. You should check with your doctor or healthcare provider about risks to your unborn child of any medication taken during pregnancy.

2. While breastfeeding

If you are breastfeeding, consult your doctor or healthcare provider before starting oral contraceptives. Some of the drug will be passed on to the child in the milk. A few adverse effects on the child have been reported, including yellowing of the skin (jaundice) and breast enlargement. In addition, oral contraceptives may decrease the amount and quality of your milk. If possible, do not use oral contraceptives while breastfeeding. You should use another method of contraception since breastfeeding provides only partial protection from becoming pregnant and this partial protection decreases significantly as you breastfeed for longer periods of time. You should consider starting oral contraceptives only after you have weaned your child completely.

3. Laboratory tests

If you are scheduled for any laboratory tests, tell your doctor or healthcare provider you are taking birth control pills. Certain blood tests may be affected by birth control pills.

4. Drug interactions

Certain drugs may interact with birth control pills to make them less effective in preventing pregnancy or cause an increase in breakthrough bleeding. Such drugs include rifampin, drugs used for epilepsy such as barbiturates (for example, phenobarbital), phenytoin (Dilantin® is one brand of this drug), phenylbutazone (Butazolidin® is one brand), and possibly certain antibiotics. You may need to use additional contraception when you take drugs which can make oral contraceptives less effective.

Birth control pills may interact with lamotrigine, an anticonvulsant used for epilepsy. This may increase the risk of seizures, so your physician may need to adjust the dose of lamotrigine.

Some medicines may make birth control pill less effective, including:

- Barbiturates
- Bosentan
- Carbamazepine
- Felbamate
- Griseofulvin
- Oxcarbazepine
- Phenytoin
- Rifampin
- St. John’s wort
- Topiramate

As with all prescription products, you should notify your healthcare provider of any other medicines and herbal products you are taking. You may need to use a barrier contraceptive when you take drugs or products that can make birth control pills less effective.

5. Sexually transmitted infections

This product (like all oral contraceptives) is intended to prevent pregnancy. It does not protect against transmission of HIV (AIDS) and other sexually transmitted infections such as chlamydia, genital herpes, genital warts, gonorrhea, hepatitis B, and syphilis.

HOW TO TAKE THE PILL

IMPORTANT POINTS TO REMEMBER

BEFORE YOU START TAKING YOUR PILLS:

1. BE SURE TO READ THESE DIRECTIONS:

Before you start taking your pills.

Anytime you are not sure what to do.

2. THE RIGHT WAY TO TAKE THE PILL IS TO TAKE ONE PILL EVERY DAY AT THE SAME TIME.

If you miss pills you could get pregnant. This includes starting the pack late.

The more pills you miss, the more likely you are to get pregnant.

3. MANY WOMEN HAVE SPOTTING OR LIGHT BLEEDING, OR MAY FEEL SICK TO THEIR STOMACH DURING THE FIRST 1 TO 3 PACKS OF PILLS.

If you feel sick to your stomach, do not stop taking the pill. The problem will usually go away. If it doesn't go away, check with your doctor or healthcare provider.

4. MISSING PILLS CAN ALSO CAUSE SPOTTING OR LIGHT BLEEDING, even when you make up these missed pills.

On the days you take 2 pills to make up for missed pills, you could also feel a little sick to your stomach.

5. IF YOU HAVE VOMITING OR DIARRHEA, for any reason, or IF YOU TAKE SOME MEDICINES, including some antibiotics, your pills may not work as well.

Use a back-up method (such as condoms, foam, or sponge) until you check with your doctor or healthcare provider.

6. IF YOU HAVE TROUBLE REMEMBERING TO TAKE THE PILL, talk to your doctor or healthcare provider about how to make pill-taking easier or about using another method of birth control.

7. IF YOU HAVE ANY QUESTIONS OR ARE UNSURE ABOUT THE INFORMATION IN THIS LEAFLET, call your doctor or healthcare provider.

BEFORE YOU START TAKING YOUR PILLS

1. DECIDE WHAT TIME OF DAY YOU WANT TO TAKE YOUR PILL.

It is important to take it at about the same time every day.

2. LOOK AT YOUR PILL PACK: IT WILL HAVE 28 PILLS:

This 28-pill pack has 26 “active” [white to off-white and light yellow to yellow] pills (with hormones) and 2 “inactive” [pale green to yellowish green] pills (without hormones).

3. ALSO FIND:

1. where on the pack to start taking the pills,
2. in what order to take the pills (follow the arrows) and
3. the week numbers as shown in the picture below.

4. BE SURE YOU HAVE READY AT ALL TIMES:

ANOTHER KIND OF BIRTH CONTROL (such as condoms, foam, or sponge) to use as a back-up in case you miss pills.

AN EXTRA, FULL PILL PACK.

WHEN TO START THE FIRST PACK OF PILLS

You have a choice of which day to start taking your first pack of pills. Decide with your doctor or healthcare provider which is the best day for you. Pick a time of day which will be easy to remember.

DAY 1 START:

1. Pick the day label strip that starts with the first day of your period (this is the day you start bleeding or spotting, even if it is almost midnight when the bleeding begins).

2. Place this day label strip in the cycle tablet blister over the area that has the days of the week (starting with Sunday) imprinted.

Note: If the first day of your period is a Sunday, you can skip steps #1 and #2.

3. Take the first “active” [white to off-white] pill of the first pack during the first 24 hours of your period.

4. You will not need to use a back-up method of birth control, since you are starting the pill at the beginning of your period.

SUNDAY START:

1. Take the first “active” [white to off-white] pill of the first pack on the Sunday after your period starts, even if you are still bleeding. If your period begins on Sunday, start the pack that same day.
2. Use another method of birth control as a back-up method if you have sex anytime from the Sunday you start your first pack until the next Sunday (7 days). Condoms, foam, or the sponge are good back-up methods of birth control.

WHAT TO DO DURING THE MONTH

1. TAKE ONE PILL AT THE SAME TIME EVERY DAY UNTIL THE PACK IS EMPTY.

Do not skip pills even if you are spotting or bleeding between monthly periods or feel sick to your stomach (nausea).

Do not skip pills even if you do not have sex very often.

2. WHEN YOU FINISH A PACK OR SWITCH YOUR BRAND OF PILLS:

21 pills: Wait 7 days to start the next pack. You will probably have your period during that week. Be sure that no more than 7 days pass between 21-day packs.

28 pills: Start the next pack on the day after your last pill. Do not wait any days between packs.

WHAT TO DO IF YOU MISS PILLS

If you MISS 1 “active” [white to off-white] pill:

1. Take it as soon as you remember. Take the next pill at your regular time. This means you take 2 pills in 1 day.
2. You do not need to use a back-up birth control method if you have sex.

If you MISS 2 “active” [white to off-white] pills in a row in WEEK 1 OR WEEK 2 of your pack:

1. Take 2 pills on the day you remember and 2 pills the next day.
2. Then take 1 pill a day until you finish the pack.
3. You MAY BECOME PREGNANT if you have sex in the 7 days after you miss pills.

You MUST use another birth control method (such as condoms, foam, or sponge) as a back-up method for those 7 days.

If you MISS 2 “active” [white to off-white] pills in a row in WEEK 3:

1. If you are a Day 1 Starter:

THROW OUT the rest of the pill pack and start a new pack that same day.

If you are a Sunday Starter:

Keep taking 1 pill every day until Sunday.

On Sunday, THROW OUT the rest of the pack and start a new pack of pills that same day.

2. You may not have your period this month but this is expected. However, if you miss your period 2 months in a row, call your doctor or healthcare provider because you might be pregnant.

3. You MAY BECOME PREGNANT if you have sex in the 7 days after you miss pills. You MUST use another birth control method (such as condoms, foam, or sponge) as a back-up method for those 7 days.

If you MISS 3 OR MORE “active” [white to off-white] pills in a row (during the first 3 weeks):

1. If you are a Day 1 Starter:

THROW OUT the rest of the pill pack and start a new pack that same day.

If you are a Sunday Starter:

Keep taking 1 pill every day until Sunday.

On Sunday, THROW OUT the rest of the pack and start a new pack of pills that same day.

2. You may not have your period this month but this is expected. However, if you miss your period 2 months in a row, call your doctor or healthcare provider because you might be pregnant.

3. You MAY BECOME PREGNANT if you have sex in the 7 days after you miss pills. You MUST use another birth control method (such as condoms, foam, or sponge) as a back-up method for those 7 days.

A REMINDER FOR THOSE ON 28-DAY PACKS

If you forget any of the 2 [pale green to yellowish green] or 5 [light yellow to yellow] pills in Week 4:

THROW AWAY the pills you missed.

Keep taking 1 pill each day until the pack is empty.

You do not need a back-up method.

FINALLY, IF YOU ARE STILL NOT SURE WHAT TO DO ABOUT THE PILLS YOU HAVE MISSED:

Use a BACK-UP METHOD anytime you have sex.

KEEP TAKING ONE “ACTIVE” [WHITE TO OFF-WHITE] PILL EACH DAY until you can reach your doctor or healthcare provider.

PREGNANCY DUE TO PILL FAILURE

The incidence of pill failure resulting in pregnancy is approximately one percent (i.e., one pregnancy per 100 women per year) if taken every day as directed, but more typical failure rates are about 5%. If failure does occur, the risk to the fetus is minimal.

PREGNANCY AFTER STOPPING THE PILL

There may be some delay in becoming pregnant after you stop using oral contraceptives, especially if you had irregular menstrual cycles before you used oral contraceptives. It may be advisable to postpone conception until you begin menstruating regularly once you have stopped taking the pill and desire pregnancy.

There does not appear to be any increase in birth defects in newborn babies when pregnancy occurs soon after stopping the pill.

OVERDOSAGE

Serious ill effects have not been reported following ingestion of large doses of oral contraceptives by young children. Overdosage may cause nausea and withdrawal bleeding in females. In case of overdosage, contact your doctor, healthcare provider or pharmacist.

OTHER INFORMATION

Your doctor or healthcare provider will take a medical and family history before prescribing oral contraceptives and will examine you. The physical examination may be delayed to another time if you request it and your doctor or the healthcare provider believes that it is a good medical practice to postpone it. You should be reexamined at least once a year. Be sure to inform your doctor or healthcare provider if there is a family history of any of the conditions listed previously in this leaflet. Be sure to keep all appointments with your doctor or healthcare provider, because this is a time to determine if there are early signs of side effects of oral contraceptive use.

Do not use the drug for any condition other than the one for which it was prescribed. This drug has been prescribed specifically for you; do not give it to others who may want birth control pills.

HEALTH BENEFITS FROM ORAL CONTRACEPTIVES

In addition to preventing pregnancy, use of combination oral contraceptives may provide certain benefits. They are:

- menstrual cycles may become more regular.
- blood flow during menstruation may be lighter and less iron may be lost. Therefore, anemia due to iron deficiency is less likely to occur.
- pain or other symptoms during menstruation may be encountered less frequently.
- ectopic (tubal) pregnancy may occur less frequently.
- non-cancerous cysts or lumps in the breast may occur less frequently.
- acute pelvic inflammatory disease may occur less frequently.
- oral contraceptive use may provide some protection against developing two forms of cancer: cancer of the ovaries and cancer of the lining of the uterus.

If you want more information about birth control pills, ask your doctor, healthcare provider, or pharmacist. They have a more technical leaflet called the Prescribing Information which you may wish to read.

Distributed by:

Glenmark Pharmaceuticals Inc., USA

Elmwood Park, NJ 07407

Questions? 1 (888) 721-7115

www.glenmarkpharma-us.com

May 2025